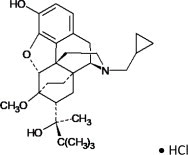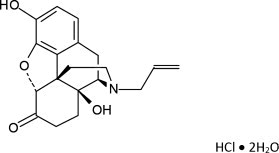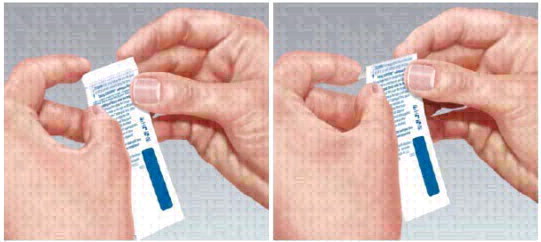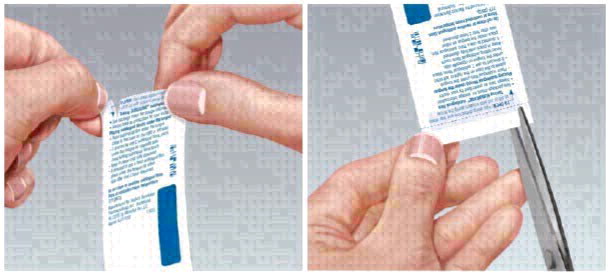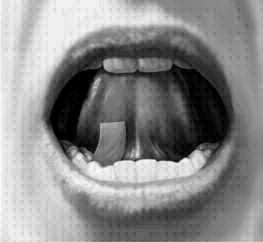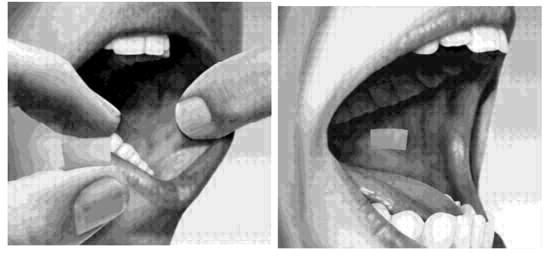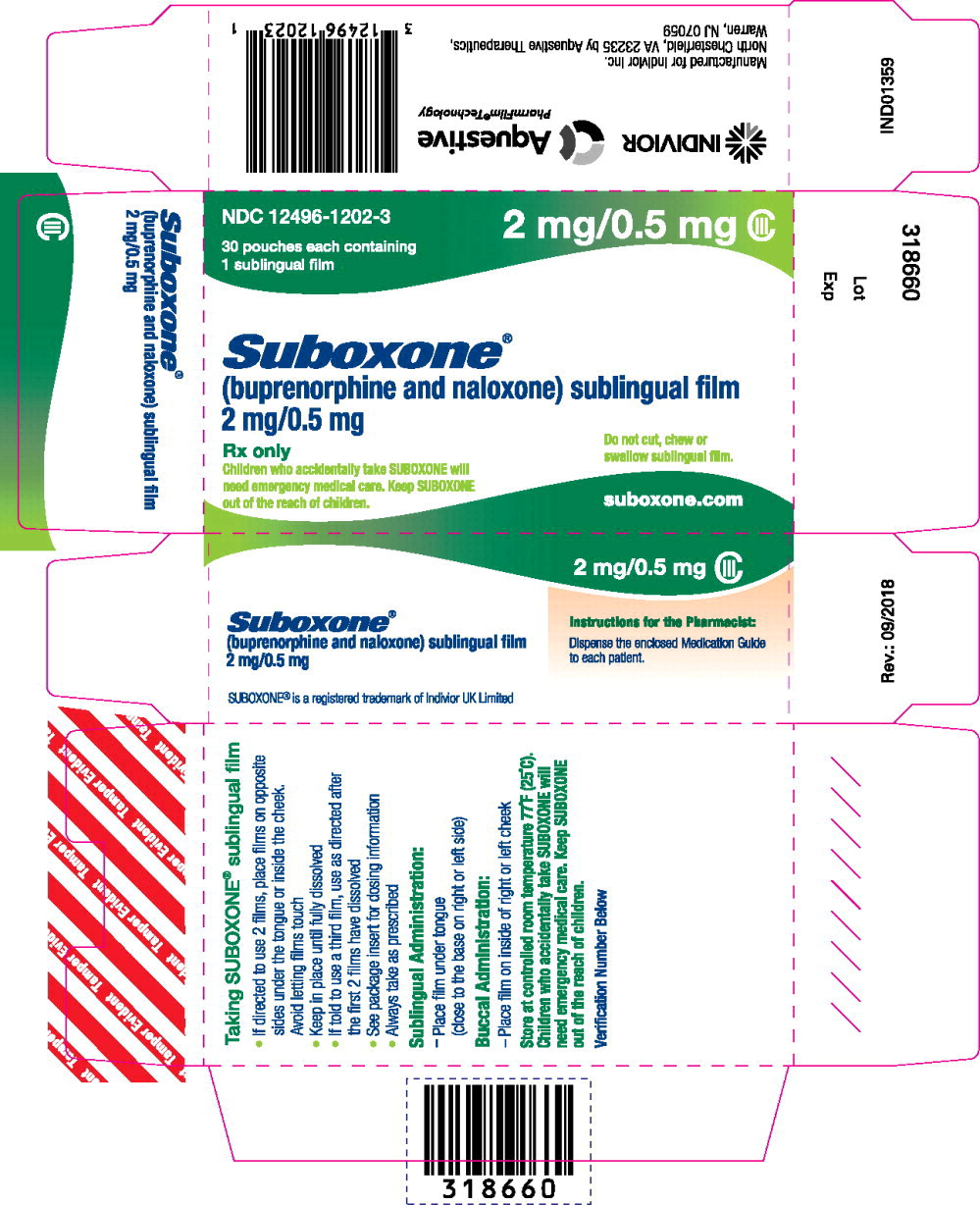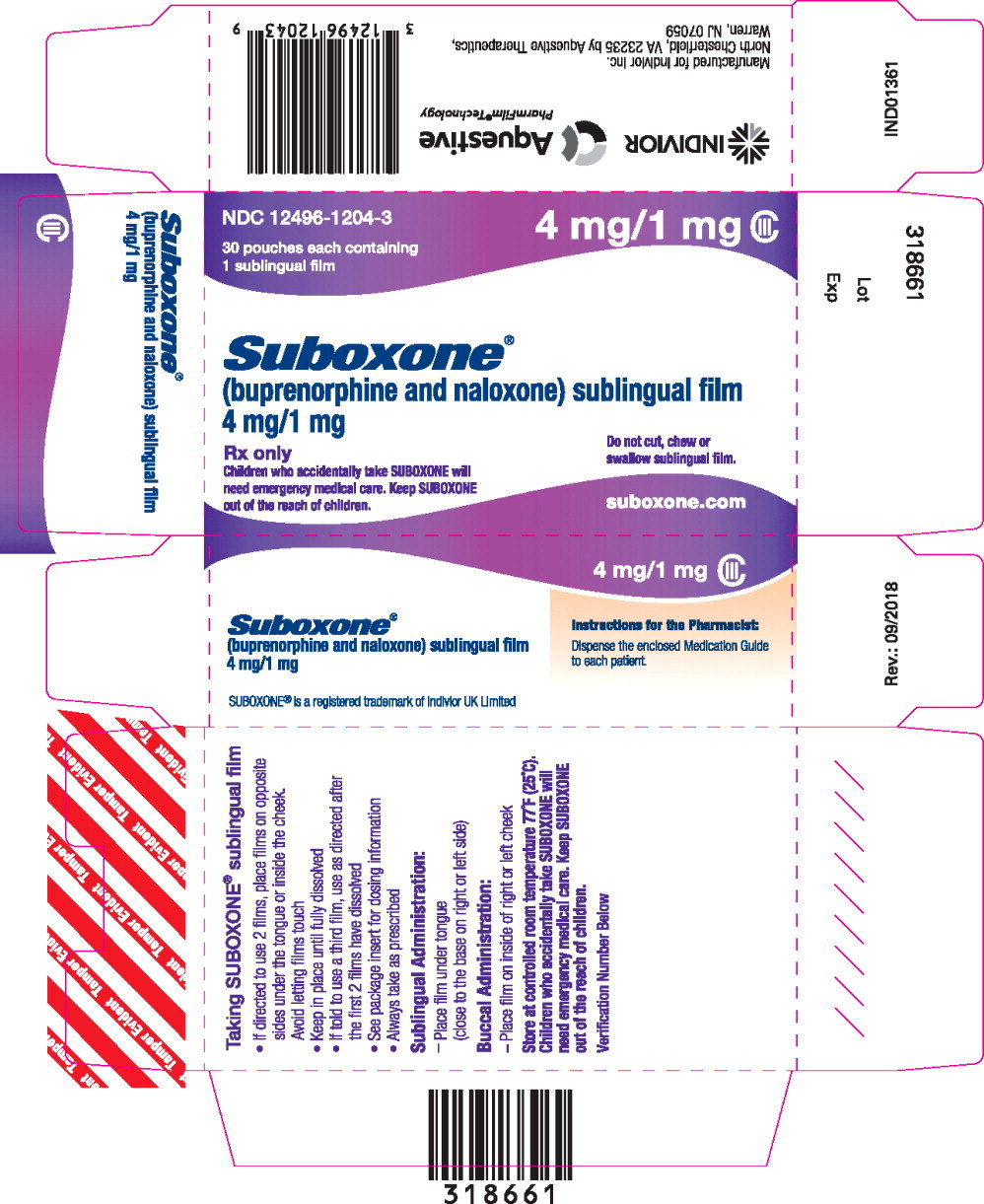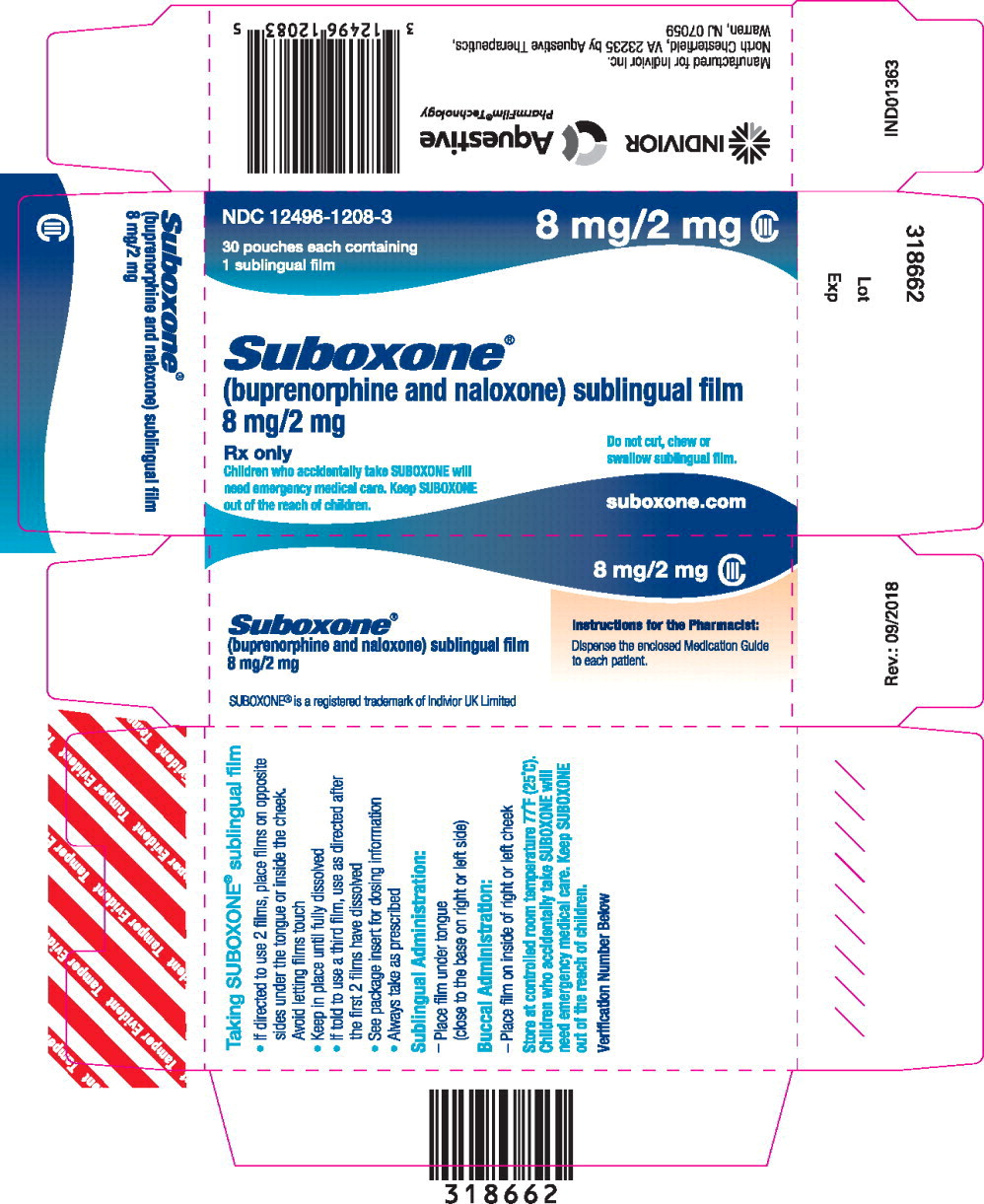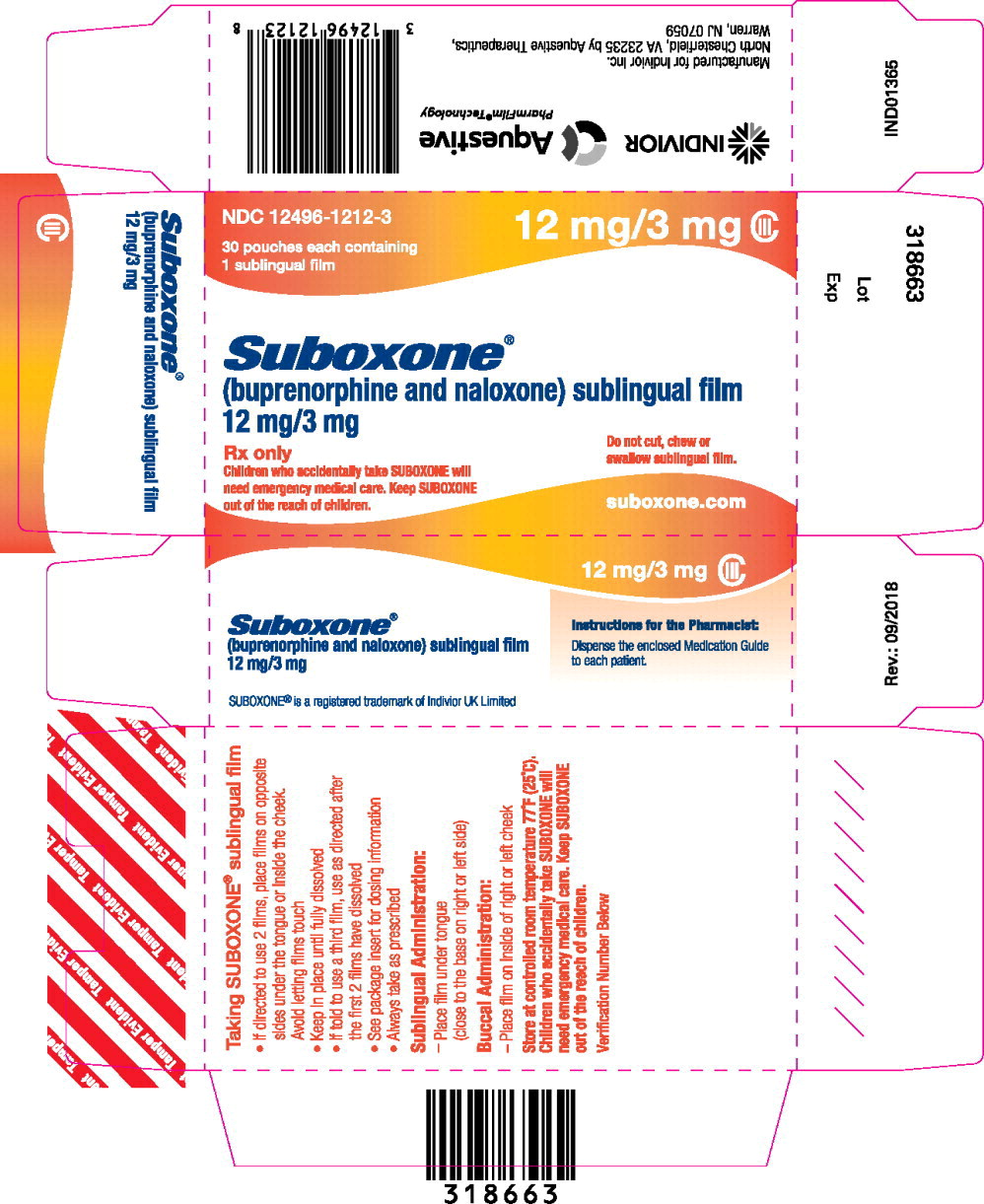 DRUG LABEL: Suboxone
NDC: 12496-1202 | Form: FILM, SOLUBLE
Manufacturer: INDIVIOR INC.
Category: prescription | Type: HUMAN PRESCRIPTION DRUG LABEL
Date: 20251222
DEA Schedule: CIII

ACTIVE INGREDIENTS: BUPRENORPHINE HYDROCHLORIDE 2 mg/1 1; NALOXONE HYDROCHLORIDE 0.5 mg/1 1
INACTIVE INGREDIENTS: POLYETHYLENE GLYCOL, UNSPECIFIED; HYPROMELLOSES; MALTITOL; ACESULFAME POTASSIUM; CITRIC ACID MONOHYDRATE; SODIUM CITRATE; FD&C YELLOW NO. 6

HIGHLIGHTS OF PRESCRIBING INFORMATION

These highlights do not include all the information needed to use SUBOXONE sublingual film safely and effectively. See full prescribing information for SUBOXONE sublingual film.
SUBOXONE® (buprenorphine and naloxone) sublingual film, for sublingual or buccal use, CIII
Initial U.S. Approval: 2002

RECENT MAJOR CHANGES

Dosage and Administration (2.2) | 12/2025
Dosage and Administration (2.4) | 05/2025
Warnings and Precautions (5.2, 5.3) | 12/2025

1 INDICATIONS AND USAGE

SUBOXONE® sublingual film contains buprenorphine, a partial‐opioid agonist, and naloxone, an opioid antagonist, and is indicated for treatment of opioid dependence. (1)

SUBOXONE sublingual film should be used as part of a complete treatment plan that includes counseling and psychosocial support. (1)

2 DOSAGE AND ADMINISTRATION

- Administer SUBOXONE sublingual film as a single daily dose. (2.1)
- Strongly consider recommending or prescribing an opioid overdose reversal agent (e.g., naloxone, nalmefene) at the time SUBOXONE sublingual film is initiated or renewed because patients being treated for opioid use disorder have the potential for relapse, putting them at risk for opioid overdose. (2.2)
- To avoid precipitating withdrawal, induction with SUBOXONE sublingual film should be undertaken when objective and clear signs of withdrawal are evident and SUBOXONE sublingual film should be administered in divided doses when used as initial treatment. (2.3)
- For patients dependent on short‐acting opioid products who are in opioid withdrawal; on Day 1, administer up to 8 mg/2 mg SUBOXONE sublingual film (in divided doses). On Day 2, administer up to 16 mg/4 mg of SUBOXONE sublingual film as a single dose. (2.3)
- For patients dependent on methadone or long‐acting opioid products, induction onto sublingual buprenorphine monotherapy is recommended on Days 1 and 2 of treatment. (2.3)
- The maintenance dose of SUBOXONE sublingual film is generally in the range of 4 mg/1 mg to 24 mg/6 mg per day and should be based on clinical response. (2.4)
- Sublingual Administration: Place one film under the tongue, close to the base on the left or right side, and allow to completely dissolve. Buccal Administration: Place one film on the inside of the left or right cheek and allow to completely dissolve. (2.5)
- SUBOXONE sublingual film must be administered whole. Do not cut, chew, or swallow SUBOXONE sublingual film (2.5)
- When discontinuing treatment, gradually taper to avoid signs and symptoms of withdrawal. (2.8)

3 DOSAGE FORMS AND STRENGTHS

Sublingual film:

- buprenorphine 2 mg/ naloxone 0.5 mg,
- buprenorphine 4 mg/ naloxone 1 mg,
- buprenorphine 8 mg/ naloxone 2 mg and
- buprenorphine 12 mg/ naloxone 3 mg. (3)

4 CONTRAINDICATIONS

Hypersensitivity to buprenorphine or naloxone. (4)

5 WARNINGS AND PRECAUTIONS

- Addiction, Abuse, and Misuse: Buprenorphine can be abused in a similar manner to other opioids. Monitor patients for conditions indicative of diversion or progression of opioid dependence and addictive behaviors. Multiple refills should not be prescribed early in treatment or without appropriate patient follow-up visits. (5.1)
- Respiratory Depression: Life-threatening respiratory depression and death have occurred in association with buprenorphine use. Warn patients of the potential danger of self-administration of benzodiazepines or other CNS depressants while under treatment with SUBOXONE sublingual film. (5.2, 5.3)
- Unintentional Pediatric Exposure: Store SUBOXONE sublingual film safely out of the sight and reach of children. Buprenorphine can cause severe, possibly fatal, respiratory depression in children. (5.4)
- Neonatal Opioid Withdrawal Syndrome: Neonatal opioid withdrawal syndrome (NOWS) is an expected and treatable outcome of prolonged use of opioids during pregnancy (5.5)
- Adrenal Insufficiency: If diagnosed, treat with physiologic replacement of corticosteroids, and wean patient off of the opioid. (5.6)
- Risk of Opioid Withdrawal with Abrupt Discontinuation: If treatment is temporarily interrupted or discontinued, monitor patients for withdrawal and treat appropriately. (5.7)
- Risk of Hepatitis, Hepatic Events: Monitor liver function tests prior to initiation and during treatment and evaluate suspected hepatic events. (5.8)
- Precipitation of Opioid Withdrawal Signs and Symptoms: An opioid withdrawal syndrome is likely to occur with parenteral misuse of SUBOXONE sublingual film by individuals physically dependent on full opioid agonists, or by sublingual or buccal administration before the agonist effects of other opioids have subsided. (5.10)
- Risk of Overdose in Opioid‐Naïve Patients: SUBOXONE sublingual film is not appropriate as an analgesic. There have been reported deaths of opioid naïve individuals who received a 2 mg sublingual dose. (5.11)

6 ADVERSE REACTIONS

Adverse events commonly observed with the sublingual/buccal administration of the SUBOXONE sublingual film are oral hypoesthesia, glossodynia, oral mucosal erythema, headache, nausea, vomiting, hyperhidrosis, constipation, signs and symptoms of withdrawal, insomnia, pain, and peripheral edema. (6)

To report SUSPECTED ADVERSE REACTIONS, contact Indivior Inc. at 1-877-782-6966 or FDA at 1-800-FDA-1088 or www.fda.gov/medwatch.

7 DRUG INTERACTIONS

- Benzodiazepines: Use caution in prescribing SUBOXONE sublingual film for patients receiving benzodiazepines or other CNS depressants and warn patients against concomitant self-administration/misuse. (7)
- CYP3A4 Inhibitors and Inducers: Monitor patients starting or ending CYP3A4 inhibitors or inducers for potential over- or under- dosing. (7)
- Antiretrovirals: Patients who are on chronic buprenorphine treatment should have their dose monitored if NNRTIs are added to their treatment regimen. Monitor patients taking buprenorphine and atazanavir with and without ritonavir. Dose reduction of buprenorphine may be warranted (7).
- Serotonergic Drugs: Concomitant use may result in serotonin syndrome. Discontinue SUBOXONE sublingual film if serotonin syndrome is suspected. (7)

8 USE IN SPECIFIC POPULATIONS

- Lactation: Buprenorphine passes into mother's milk. (8.2)
- Geriatric Patients: Monitor for sedation and respiratory depression. (8.5)
- Moderate or Severe Hepatic Impairment: Buprenorphine/naloxone products are not recommended in patients with severe hepatic impairment and may not be appropriate for patients with moderate hepatic impairment. (8.6)

FULL PRESCRIBING INFORMATION

1 INDICATIONS AND USAGE

SUBOXONE sublingual film is indicated for treatment of opioid dependence. SUBOXONE sublingual film should be used as part of a complete treatment plan that includes counseling and psychosocial support.

2 DOSAGE AND ADMINISTRATION

2.1 Important Dosage and Administration Information

SUBOXONE sublingual film is administered sublingually or buccally as a single daily dose.

Medication should be prescribed in consideration of the frequency of visits. Provision of multiple refills is not advised early in treatment or without appropriate patient follow‐up visits.

2.2 Patient Access to an Opioid Overdose Reversal Agent for the Emergency Treatment of Opioid Overdose

Inform patients and caregivers about opioid overdose reversal agents (e.g., naloxone, nalmefene) and discuss the importance of having access to an opioid overdose reversal agent. Because patients being treated for opioid use disorder have the potential for relapse, putting them at risk for opioid overdose, strongly consider recommending or prescribing an overdose reversal agent for the emergency treatment of opioid overdose, both when initiating and renewing treatment with SUBOXONE sublingual film. Also consider recommending or prescribing such an agent if the patient has household members (including children) or other close contacts at risk for accidental ingestion or opioid overdose [see Warnings and Precautions (5.2)].

Discuss the options for obtaining an opioid overdose reversal agent (e.g., prescription, over-the-counter, or as part of a community-based program) [see Warnings and Precautions (5.2)].

There are important differences among the opioid overdose reversal agents, such as route of administration, product strength, approved patient age range, and pharmacokinetics. Be familiar with these differences, as outlined in the approved labeling for those products, prior to recommending or prescribing such an agent.

Advise patients and caregivers that opioid overdose reversal agents, such as naloxone or nalmefene, may also be administered for a known or suspected overdose with buprenorphine itself. Higher than normal doses and repeated administration of an opioid overdose reversal agent may be necessary due to the long duration of action of buprenorphineand its affinity for the mu-opioid receptor [see Overdosage (10)].

2.3 Induction

Prior to induction, consideration should be given to the type of opioid dependence (i.e., long‐ or short‐acting opioid products), the time since last opioid use, and the degree or level of opioid dependence.

Patients dependent on heroin or other short‐acting opioid products

Patients dependent on heroin or other short‐acting opioid products may be inducted with either SUBOXONE sublingual film or with sublingual buprenorphine monotherapy. At treatment initiation, the first dose of SUBOXONE sublingual film should be administered when objective signs of moderate opioid withdrawal appear, not less than six hours after the patient last used opioids.

It is recommended that an adequate treatment dose, titrated to clinical effectiveness, be achieved as rapidly as possible. In some studies, a too‐gradual induction over several days led to a high rate of drop‐out of buprenorphine patients during the induction period.

On Day 1, an induction dosage of up to 8 mg/2 mg SUBOXONE sublingual film is recommended. Clinicians should start with an initial dose of 2 mg/0.5 mg or 4 mg/1 mg buprenorphine/naloxone and may titrate upwards in 2 or 4 mg increments of buprenorphine, at approximately 2‐hour intervals, under supervision, to 8 mg/2 mg buprenorphine/naloxone based on the control of acute withdrawal symptoms.

On Day 2, a single daily dose of up to 16 mg/4 mg SUBOXONE sublingual film is recommended.

Because the exposure to naloxone is somewhat higher after buccal than after sublingual administration, it is recommended that the sublingual site of administration be used during induction to minimize exposure to naloxone, to reduce the risk of precipitated withdrawal.

Patients dependent on methadone or long‐acting opioid products

Patients dependent upon methadone or long‐acting opioid products may be more susceptible to precipitated and prolonged withdrawal during induction than those on short‐acting opioid products.

Buprenorphine/naloxone combination products have not been evaluated in adequate and well‐controlled studies for induction in patients who are physically dependent on long‐acting opioid products, and the naloxone in these combination products is absorbed in small amounts by the sublingual route and could cause worse precipitated and prolonged withdrawal. For this reason, buprenorphine monotherapy is recommended in patients taking long‐acting opioids when used according to approved administration instructions. Following induction, the patient may then be transitioned to once‐daily SUBOXONE sublingual film.

2.4 Maintenance

- For maintenance, SUBOXONE sublingual film may be administered buccally or sublingually.
- The dosage of SUBOXONE sublingual film from Day 3 onwards should be progressively adjusted in increments/decrements of 2 mg/0.5 mg or 4 mg/1 mg buprenorphine/naloxone to a level that holds the patient in treatment and suppresses opioid withdrawal signs and symptoms.
- After treatment induction to the recommended dose of 16 mg/4 mg buprenorphine/naloxone per day, dosing should be further adjusted based on the individual patient and clinical response. The maintenance dose of SUBOXONE sublingual film is generally in the range of 4 mg/1 mg buprenorphine/naloxone to 24 mg/6 mg buprenorphine/naloxone per day. Dosages higher than 24 mg/6 mg daily have not been investigated in randomized clinical trials but may be appropriate for some patients.
- When determining the prescription quantity for unsupervised administration, consider the patient's level of stability, the security of his or her home situation, and other factors likely to affect the ability to manage supplies of take‐home medication.
- There is no maximum recommended duration of maintenance treatment. Patients may require treatment indefinitely and should continue for as long as patients are benefiting and the use of SUBOXONE sublingual film contributes to the intended treatment goals.

2.5 Method of Administration

SUBOXONE sublingual film must be administered whole. Do not cut, chew, or swallow SUBOXONE sublingual film. Advise patients not to eat or drink anything until the film is completely dissolved.

Sublingual Administration

Place one film under the tongue, close to the base on the left or right side. If an additional film is necessary to achieve the prescribed dose, place an additional film sublingually on the opposite side from the first film. Place the film in a manner to minimize overlapping as much as possible. The film must be kept under the tongue until the film is completely dissolved. If a third film is necessary to achieve the prescribed dose, place it under the tongue on either side after the first 2 films have dissolved.

Buccal Administration

Place one film on the inside of the right or left cheek. If an additional film is necessary to achieve the prescribed dose, place an additional film on the inside of the opposite cheek. The film must be kept on the inside of the cheek until the film is completely dissolved. If a third film is necessary to achieve the prescribed dose, place it on the inside of the right or left cheek after the first two films have dissolved.

SUBOXONE sublingual film should NOT be moved after placement.

To ensure consistency in bioavailability, patients should follow the same manner of dosing with continued use of the product. Proper administration technique should be demonstrated to the patient.

Advise patients to do the following after the product has completely dissolved in the oral mucosa: take a sip of water, swish gently around the teeth and gums, and swallow. Advise patients to wait for at least one hour after taking SUBOXONE before brushing teeth [see Warnings and Precautions (5.13), Postmarketing Experience (6.2), Information for Patients (17), and the Medication Guide].

2.6 Clinical Supervision

Treatment should be initiated with supervised administration, progressing to unsupervised administration as the patient's clinical stability permits. SUBOXONE sublingual film is subject to diversion and abuse. When determining the prescription quantity for unsupervised administration, consider the patient's level of stability, the security of his or her home situation, and other factors likely to affect the ability to manage supplies of take‐home medication.

Ideally patients should be seen at reasonable intervals (e.g., at least weekly during the first month of treatment) based upon the individual circumstances of the patient. Medication should be prescribed in consideration of the frequency of visits. Provision of multiple refills is not advised early in treatment or without appropriate patient follow‐up visits. Periodic assessment is necessary to determine compliance with the dosing regimen, effectiveness of the treatment plan, and overall patient progress.

Once a stable dosage has been achieved and patient assessment (e.g., urine drug screening) does not indicate illicit drug use, less frequent follow‐up visits may be appropriate. A once‐monthly visit schedule may be reasonable for patients on a stable dosage of medication who are making progress toward their treatment objectives. Continuation or modification of pharmacotherapy should be based on the healthcare provider's evaluation of treatment outcomes and objectives such as:

1. Absence of medication toxicity.
2. Absence of medical or behavioral adverse effects.
3. Responsible handling of medications by the patient.
4. Patient's compliance with all elements of the treatment plan (including recovery‐oriented activities, psychotherapy, and/or other psychosocial modalities).
5. Abstinence from illicit drug use (including problematic alcohol and/or benzodiazepine use).

If treatment goals are not being achieved, the healthcare provider should re‐evaluate the appropriateness of continuing the current treatment.

2.7 Unstable Patients

Healthcare providers will need to decide when they cannot appropriately provide further management for particular patients. For example, some patients may be abusing or dependent on various drugs, or unresponsive to psychosocial intervention such that the healthcare provider does not feel that he/she has the expertise to manage the patient. In such cases, the healthcare provider may want to assess whether to refer the patient to a specialist or more intensive behavioral treatment environment. Decisions should be based on a treatment plan established and agreed upon with the patient at the beginning of treatment.

Patients who continue to misuse, abuse, or divert buprenorphine products or other opioids should be provided with, or referred to, more intensive and structured treatment.

2.8 Discontinuing Treatment

The decision to discontinue therapy with SUBOXONE sublingual film after a period of maintenance should be made as part of a comprehensive treatment plan. Advise patients of the potential to relapse to illicit drug use following discontinuation of opioid agonist/partial agonist medication‐assisted treatment. Taper patients to reduce the occurrence of opioid withdrawal signs and symptoms [See Warnings and Precautions (5.7)].

2.9 Switching Between Buprenorphine or Buprenorphine and Naloxone Sublingual Tablets and SUBOXONE Sublingual Film

Patients being switched between buprenorphine and naloxone or buprenorphine only sublingual tablets and SUBOXONE sublingual film should be started on the same dosage of the previously administered product. However, dosage adjustments may be necessary when switching between buprenorphine products. Not all strengths and combinations of the SUBOXONE sublingual films are bioequivalent to SUBOXONE® sublingual tablets as observed in pharmacokinetic studies [see Clinical Pharmacology (12.3)]. Therefore, systemic exposures of buprenorphine and naloxone may be different when patients are switched from tablets to film or vice‐versa. Patients should be monitored for symptoms related to over‐dosing or under‐dosing.

2.10 Switching Between SUBOXONE Sublingual Film Strengths

As indicated in Table 1, the sizes and the compositions of the four units of SUBOXONE sublingual films, i.e., 2 mg/0.5 mg, 4 mg/1 mg, 8 mg/2 mg and the 12 mg/3 mg units, are different from one another. If patients switch between various combinations of lower and higher strength units of SUBOXONE sublingual films to obtain the same total dose, (e.g., from three 4 mg/1 mg units to a single 12 mg/3 mg unit, or vice‐versa), systemic exposures of buprenorphine and naloxone may be different and patients should be monitored for over‐dosing or under‐dosing. For this reason, pharmacist should not substitute one or more film strengths for another without approval of the prescriber.

Table 1. Comparison of Available SUBOXONE Sublingual Film Strengths by Dimensions and Drug Concentrations.
SUBOXONE sublingual film unit strength (buprenorphine/naloxone) | SUBOXONE sublingual film unit dimensions | Buprenorphine Concentration % (w/w) | Naloxone Concentration % (w/w)
2 mg/0.5 mg | 22.0 mm x 12.8 mm | 5.4 | 1.53
4 mg/1 mg (2 times the length of the 2 mg/0.5 mg unit) | 22.0 mm x 25.6 mm | 5.4 | 1.53
8 mg/2 mg | 22.0 mm x 12.8 mm | 17.2 | 4.88
12 mg/3 mg (1.5 times the length of the 8 mg/2 mg unit) | 22.0 mm X 19.2 mm | 17.2 | 4.88

2.11 Switching Between Sublingual and Buccal Sites of Administration

The systemic exposure of buprenorphine between buccal and sublingual administration of SUBOXONE sublingual film is similar. Therefore, once induction is complete, patients can switch between buccal and sublingual administration without significant risk of under or overdosing.

3 DOSAGE FORMS AND STRENGTHS

SUBOXONE sublingual film is supplied as an orange rectangular film with a white printed logo in four dosage strengths:

- Buprenorphine 2 mg/naloxone 0.5 mg,
- Buprenorphine 4 mg/naloxone 1 mg,
- Buprenorphine 8 mg/naloxone 2 mg and
- Buprenorphine 12 mg/naloxone 3 mg

4 CONTRAINDICATIONS

SUBOXONE sublingual film is contraindicated in patients with a history of hypersensitivity to buprenorphine or naloxone as serious adverse reactions, including anaphylactic shock, have been reported [see Warnings and Precautions (5.9)].

5 WARNINGS AND PRECAUTIONS

5.1 Addiction, Abuse, and Misuse

SUBOXONE sublingual film contains buprenorphine, a schedule III controlled substance that can be abused in a manner similar to other opioids, legal or illicit. Prescribe and dispense buprenorphine with appropriate precautions to minimize risk of misuse, abuse, or diversion, and ensure appropriate protection from theft, including in the home. Clinical monitoring appropriate to the patient's level of stability is essential. Multiple refills should not be prescribed early in treatment or without appropriate patient follow‐up visits [see Drug Abuse and Dependence (9.2)].

5.2 Risk of Life-Threatening Respiratory and Central Nervous System (CNS) Depression

Buprenorphine has been associated with life‐threatening respiratory depression and death. Many, but not all, postmarketing reports regarding coma and death involved misuse by self‐injection or were associated with the concomitant use of buprenorphine and benzodiazepines or other CNS depressants, including alcohol. Warn patients of the potential danger of self‐administration of benzodiazepines or other CNS depressants while under treatment with SUBOXONE sublingual film [see Warnings and Precautions (5.3), Drug Interactions (7)].

Use SUBOXONE sublingual film with caution in patients with compromised respiratory function (e.g., chronic obstructive pulmonary disease, cor pulmonale, decreased respiratory reserve, hypoxia, hypercapnia, or pre-existing respiratory depression).

Educate patients and caregivers on how to recognize respiratory depression and emphasize the importance of calling 911 or getting emergency medical help right away in the event of a known or suspected overdose [see Patient Counseling Information (17)].

Opioids can cause sleep-related breathing disorders including central sleep apnea (CSA) and sleep-related hypoxemia. Opioid use increases the risk of CSA in a dose-dependent fashion. In patients who present with CSA, consider decreasing the opioid dosage using best practices for opioid taper [see Dosage and Administration (2.8)].

Patient Access to an Opioid Overdose Reversal Agent for the Emergency Treatment of Opioid Overdose

Inform patients and caregivers about opioid overdose reversal agents (e.g., naloxone, nalmefene) and discuss the importance of having access to an opioid overdose reversal agent.

Because patients being treated for opioid use disorder have the potential for relapse, putting them at risk for opioid overdose, strongly consider recommending or prescribing an opioid overdose reversal agent for the emergency treatment of an opioid overdose, both when initiating and renewing treatment with SUBOXONE sublingual film. Also consider recommending or prescribing such an agent if the patient has household members (including children) or other close contacts at risk for accidental ingestion or opioid overdose [see Dosage and Administration (2.2)].

Discuss the options for obtaining an opioid overdose reversal agent (e.g., prescription, over-the-counter, or as part of a community-based program).

There are important differences among the opioid overdose reversal agents, such as route of administration, product strength, approved patient age range, and pharmacokinetics. Be familiar with these differences, as outlined in the approved labeling for those products, prior to recommending or prescribing such an agent.

Advise patients and caregivers that an opioid overdose reversal agent, such as naloxone or nalmefene, may also be administered for a known or suspected overdose with buprenorphine itself. Higher than normal doses and repeated administration of an opioid overdose reversal agent may be necessary due to the long duration of action of buprenorphine and its affinity for the mu-opioid receptor [see Overdosage (10)].

Educate patients and caregivers on how to recognize respiratory depression, and how to use an opioid overdose reversal agent for the emergency treatment of opioid overdose. Emphasize the importance of calling 911 or getting emergency medical help, even if an opioid overdose reversal agent is administered.

5.3 Managing Risks from Concomitant Use of Benzodiazepines or Other CNS Depressants

Concomitant use of buprenorphine and benzodiazepines and/or other CNS depressants (e.g., alcohol, non-benzodiazepine sedative/hypnotics, anxiolytics, tranquilizers, muscle relaxants, general anesthetics, antipsychotics, gabapentinoids [gabapentin or pregabalin], and other opioids) increases the risk of adverse reactions including overdose, respiratory depression, and death. Medication-assisted treatment of opioid use disorder, however, should not be categorically denied to patients taking these drugs. Prohibiting or creating barriers to treatment can pose an even greater risk of morbidity and mortality due to the opioid use disorder alone.

As a routine part of orientation to buprenorphine treatment, educate patients about the risks of concomitant use of benzodiazepines, sedatives, opioid analgesics, and alcohol.

Develop strategies to manage use of prescribed or illicit benzodiazepines or other CNS depressants at initiation of buprenorphine treatment, or if it emerges as a concern during treatment. Adjustments to induction procedures and additional monitoring may be required. There is no evidence to support dose limitations or arbitrary caps of buprenorphine as a strategy to address benzodiazepine use in buprenorphine‐treated patients. However, if a patient is sedated at the time of buprenorphine dosing, delay or omit the buprenorphine dose if appropriate.

Cessation of benzodiazepines or other CNS depressants is preferred in most cases of concomitant use. In some cases, monitoring in a higher level of care for taper may be appropriate. In others, gradually tapering a patient off of a prescribed benzodiazepine or other CNS depressant or decreasing to the lowest effective dose may be appropriate.

For patients in buprenorphine treatment, benzodiazepines are not the treatment of choice for anxiety or insomnia. Before co‐prescribing benzodiazepines, ensure that patients are appropriately diagnosed and consider alternative medications and non‐pharmacologic treatments to address anxiety or insomnia. Ensure that other healthcare providers prescribing benzodiazepines or other CNS depressants are aware of the patient's buprenorphine treatment and coordinate care to minimize the risks associated with concomitant use.

If concomitant use is warranted, strongly consider recommending or prescribing an opioid overdose reversal agent, as is recommended for all patients on buprenorphine treatment for opioid use disorder [see Warnings and Precautions (5.2)].

In addition, take measures to confirm that patients are taking their medications as prescribed and are not diverting or supplementing with illicit drugs. Toxicology screening should test for prescribed and illicit benzodiazepines [see Drug Interactions (7)].

5.4 Unintentional Pediatric Exposure

Buprenorphine can cause severe, possibly fatal, respiratory depression in children who are accidentally exposed to it. Store buprenorphine‐containing medications safely out of the sight and reach of children and destroy any unused medication appropriately [see Patient Counseling Information (17)].

5.5 Neonatal Opioid Withdrawal Syndrome

Neonatal opioid withdrawal syndrome (NOWS) is an expected and treatable outcome of prolonged use of opioids during pregnancy, whether that use is medically‐authorized or illicit. Unlike opioid withdrawal syndrome in adults, NOWS may be life‐threatening if not recognized and treated in the neonate. Healthcare professionals should observe newborns for signs of NOWS and manage accordingly [see Use in Specific Populations (8.1)].

Advise pregnant women receiving opioid addiction treatment with SUBOXONE sublingual film of the risk of neonatal opioid withdrawal syndrome and ensure that appropriate treatment will be available [see Use in Specific Populations (8.1)]. This risk must be balanced against the risk of untreated opioid addiction which often results in continued or relapsing illicit opioid use and is associated with poor pregnancy outcomes. Therefore, prescribers should discuss the importance and benefits of management of opioid addiction throughout pregnancy.

5.6 Adrenal Insufficiency

Cases of adrenal insufficiency have been reported with opioid use, more often following greater than one month of use. Presentation of adrenal insufficiency may include non‐specific symptoms and signs including nausea, vomiting, anorexia, fatigue, weakness, dizziness, and low blood pressure. If adrenal insufficiency is suspected, confirm the diagnosis with diagnostic testing as soon as possible. If adrenal insufficiency is diagnosed, treat with physiologic replacement doses of corticosteroids. Wean the patient off of the opioid to allow adrenal function to recover and continue corticosteroid treatment until adrenal function recovers. Other opioids may be tried as some cases reported use of a different opioid without recurrence of adrenal insufficiency. The information available does not identify any particular opioids as being more likely to be associated with adrenal insufficiency.

5.7 Risk of Opioid Withdrawal with Abrupt Discontinuation

Buprenorphine is a partial agonist at the mu‐opioid receptor and chronic administration produces physical dependence of the opioid type, characterized by withdrawal signs and symptoms upon abrupt discontinuation or rapid taper. The withdrawal syndrome is typically milder than seen with full agonists and may be delayed in onset [see Drug Abuse and Dependence (9.3)]. When discontinuing SUBOXONE sublingual film, gradually taper the dosage [see Dosage and Administration (2.8)].

5.8 Risk of Hepatitis, Hepatic Events

Cases of cytolytic hepatitis and hepatitis with jaundice have been observed in individuals receiving buprenorphine in clinical trials and through post‐marketing adverse event reports. The spectrum of abnormalities ranges from transient asymptomatic elevations in hepatic transaminases to case reports of death, hepatic failure, hepatic necrosis, hepatorenal syndrome, and hepatic encephalopathy. In many cases, the presence of pre‐existing liver enzyme abnormalities, infection with hepatitis B or hepatitis C virus, concomitant usage of other potentially hepatotoxic drugs, and ongoing injecting drug use may have played a causative or contributory role. In other cases, insufficient data were available to determine the etiology of the abnormality. Withdrawal of buprenorphine has resulted in amelioration of acute hepatitis in some cases; however, in other cases no dose reduction was necessary. The possibility exists that buprenorphine had a causative or contributory role in the development of the hepatic abnormality in some cases. Liver function tests, prior to initiation of treatment, are recommended to establish a baseline. Periodic monitoring of liver function during treatment is also recommended. A biological and etiological evaluation is recommended when a hepatic event is suspected. Depending on the case, SUBOXONE sublingual film may need to be carefully discontinued to prevent withdrawal signs and symptoms and a return by the patient to illicit drug use, and strict monitoring of the patient should be initiated.

5.9 Hypersensitivity Reactions

Cases of hypersensitivity to buprenorphine and naloxone containing products have been reported both in clinical trials and in the post‐marketing experience. Cases of bronchospasm, angioneurotic edema, and anaphylactic shock have been reported. The most common signs and symptoms include rashes, hives, and pruritus. A history of hypersensitivity to buprenorphine or naloxone is a contraindication to the use of SUBOXONE sublingual film.

5.10 Precipitation of Opioid Withdrawal Signs and Symptoms

Because it contains naloxone, SUBOXONE sublingual film is likely to produce withdrawal signs and symptoms if misused parenterally by individuals dependent on full opioid agonists such as heroin, morphine, or methadone. Because of the partial agonist properties of buprenorphine, SUBOXONE sublingual film may precipitate opioid withdrawal signs and symptoms in such persons if administered before the agonist effects of the opioid have subsided.

5.11 Risk of Overdose in Opioid Naïve Patients

There have been reported deaths of opioid ‐naïve individuals who received a 2 mg dose of buprenorphine as a sublingual tablet for analgesia. SUBOXONE sublingual film is not appropriate as an analgesic.

5.12 Use in Patients With Impaired Hepatic Function

Buprenorphine/naloxone products are not recommended in patients with severe hepatic impairment and may not be appropriate for patients with moderate hepatic impairment. The doses of buprenorphine and naloxone in this fixed‐dose combination product cannot be individually titrated, and hepatic impairment results in a reduced clearance of naloxone to a much greater extent than buprenorphine. Therefore, patients with severe hepatic impairment will be exposed to substantially higher levels of naloxone than patients with normal hepatic function. This may result in an increased risk of precipitated withdrawal at the beginning of treatment (induction) and may interfere with buprenorphine's efficacy throughout treatment. In patients with moderate hepatic impairment, the differential reduction of naloxone clearance compared to buprenorphine clearance is not as great as in subjects with severe hepatic impairment. However, buprenorphine/naloxone products are not recommended for initiation of treatment (induction) in patients with moderate hepatic impairment due to the increased risk of precipitated withdrawal. Buprenorphine/naloxone products may be used with caution for maintenance treatment in patients with moderate hepatic impairment who have initiated treatment on a buprenorphine product without naloxone. However, patients should be carefully monitored and consideration given to the possibility of naloxone interfering with buprenorphine's efficacy [see Use in Specific Populations (8.6)].

5.13 Dental Adverse Events

Cases of dental caries, some severe (i.e., tooth fracture, tooth loss), have been reported following the use of transmucosal buprenorphine-containing products. Reported events include cavities, tooth decay, dental abscesses/infection, rampant caries, tooth erosion, fillings falling out, and, in some cases, total tooth loss. Treatment for these events included tooth extraction, root canal, dental surgery, as well as other restorative procedures (i.e., fillings, crowns, implants, dentures). Multiple cases were reported in individuals without any prior history of dental problems.

Refer patients to dental care services and encourage them to have regular dental checkups while taking SUBOXONE. Educate patients to seek dental care and strategies to maintain or improve oral health while being treated with transmucosal buprenorphine-containing products. Strategies include, but are not limited to, gently rinsing the teeth and gums with water and then swallowing after SUBOXONE has been completely dissolved in the oral mucosa. Advise patients to wait for at least one hour after taking SUBOXONE before brushing teeth [see Dosing and Administration (2.5), Information for Patients (17), Medication Guide].

5.14 QTc Prolongation

Thorough QT studies with buprenorphine products have demonstrated QT prolongation ≤ 15 msec. This QTc prolongation effect does not appear to be mediated by hERG channels. Based on these two findings, buprenorphine is unlikely to be pro-arrhythmic when used alone in patients without risk factors. The risk of combining buprenorphine with other QT-prolonging agents is not known.

Consider these observations in clinical decisions when prescribing SUBOXONE sublingual film to patients with risk factors such as hypokalemia, bradycardia, recent conversion from atrial fibrillation, congestive heart failure, digitalis therapy, baseline QT prolongation, subclinical long-QT syndrome, or severe hypomagnesemia.

5.15 Impairment of Ability to Drive or Operate Machinery

SUBOXONE sublingual film may impair the mental or physical abilities required for the performance of potentially dangerous tasks such as driving a car or operating machinery, especially during treatment induction and dose adjustment. Caution patients about driving or operating hazardous machinery until they are reasonably certain that SUBOXONE sublingual film therapy does not adversely affect his or her ability to engage in such activities.

5.16 Orthostatic Hypotension

Like other opioids, SUBOXONE sublingual film may produce orthostatic hypotension in ambulatory patients.

5.17 Elevation of Cerebrospinal Fluid Pressure

Buprenorphine, like other opioids, may elevate cerebrospinal fluid pressure and should be used with caution in patients with head injury, intracranial lesions, and other circumstances when cerebrospinal pressure may be increased. Buprenorphine can produce miosis and changes in the level of consciousness that may interfere with patient evaluation.

5.18 Elevation of Intracholedochal Pressure

Buprenorphine has been shown to increase intracholedochal pressure, as do other opioids, and thus should be administered with caution to patients with dysfunction of the biliary tract.

5.19 Effects in Acute Abdominal Conditions

As with other opioids, buprenorphine may obscure the diagnosis or clinical course of patients with acute abdominal conditions.

6 ADVERSE REACTIONS

The following serious adverse reactions are described elsewhere in the labeling:

- Addiction, Abuse, and Misuse [see Warnings and Precautions (5.1)]
- Respiratory and CNS Depression [see Warnings and Precautions (5.2), (5.3)]
- Neonatal Opioid Withdrawal Syndrome [see Warnings and Precautions (5.5)]
- Adrenal Insufficiency [see Warnings and Precautions (5.6)]
- Opioid Withdrawal [see Warnings and Precautions (5.7, 5.10)]
- Hepatitis, Hepatic Events [see Warnings and Precautions (5.8)]
- Hypersensitivity Reactions [see Warnings and Precautions (5.9)]
- Orthostatic Hypotension [see Warnings and Precautions (5.16)]
- Elevation of Cerebrospinal Fluid Pressure [see Warnings and Precautions (5.17)]
- Elevation of Intracholedochal Pressure [see Warnings and Precautions (5.18)]

6.1 Clinical Trials Experience

Because clinical trials are conducted under widely varying conditions, adverse reaction rates observed in the clinical trials of a drug cannot be directly compared to rates in the clinical trials of another drug and may not reflect the rates observed in practice.

The safety of SUBOXONE sublingual film is supported by clinical trials using SUBUTEX® (buprenorphine) sublingual tablets and SUBOXONE (buprenorphine and naloxone) sublingual tablets, and other trials using buprenorphine sublingual solutions, as well as an open-label study in 194 patients treated with SUBOXONE sublingual film administered sublingually and 188 patients treated with the film administered buccally. In total, safety data from clinical studies are available from over 3000 opioid-dependent subjects exposed to buprenorphine at doses in the range used in the treatment of opioid dependence. Few differences in the adverse event profile were noted with regard to sublingually and bucally administered SUBOXONE sublingual film, SUBOXONE sublingual tablets, SUBUTEX sublingual tablets and a buprenorphine ethanolic sublingual solution.

The most common adverse event (> 1%) associated with the sublingual administration of the SUBOXONE sublingual film was oral hypoesthesia. Other adverse events were constipation, glossodynia, oral mucosal erythema, vomiting, intoxication, disturbance in attention, palpitations, insomnia, withdrawal syndrome, hyperhidrosis, and blurred vision.

The most common adverse events associated with the buccal administration were similar to those observed with sublingual administration of the film.

Other adverse event data were derived from larger, controlled studies of SUBOXONE sublingual tablets and SUBUTEX sublingual tablets and of buprenorphine sublingual solution. In a comparative study of SUBOXONE sublingual tablets and SUBUTEX sublingual tablets, adverse event profiles were similar for subjects treated with 16 mg/4 mg SUBOXONE sublingual tablets or 16 mg SUBUTEX sublingual tablets. The following adverse events were reported to occur by at least 5% of patients in a 4 week study of SUBOXONE sublingual tablets and SUBUTEX sublingual tablets.

Table 2. Adverse Events (≥ 5%) by Body System and Treatment Group in a 4 Week Study
Body System/ Adverse Event (COSTART Terminology) | SUBOXONE sublingual tablets 16 mg/4 mg/day N = 107 n (%) | SUBUTEX sublingual tablets 16 mg/day N = 103 n (%) | Placebo N = 107 n (%)
Body as a Whole
Asthenia | 7 (6.5%) | 5 (4.9%) | 7 (6.5%)
Chills | 8 (7.5%) | 8 (7.8%) | 8 (7.5%)
Headache | 39 (36.4%) | 30 (29.1%) | 24 (22.4%)
Infection | 6 (5.6%) | 12 (11.7%) | 7 (6.5%)
Pain | 24 (22.4%) | 19 (18.4%) | 20 (18.7%)
Pain abdomen | 12 (11.2%) | 12 (11.7%) | 7 (6.5%)
Pain back | 4 (3.7%) | 8 (7.8%) | 12 (11.2%)
Withdrawal syndrome | 27 (25.2%) | 19 (18.4%) | 40 (37.4%)
Cardiovascular System
Vasodilation | 10 (9.3%) | 4 (3.9%) | 7 (6.5%)
Digestive System
Constipation | 13 (12.1%) | 8 (7.8%) | 3 (2.8%)
Diarrhea | 4 (3.7%) | 5 (4.9%) | 16 (15.0%)
Nausea | 16 (15.0%) | 14 (13.6%) | 12 (11.2%)
Vomiting | 8 (7.5%) | 8 (7.8%) | 5 (4.7%)
Nervous System
Insomnia | 15 (14.0%) | 22 (21.4%) | 17 (15.9%)
Respiratory System
Rhinitis | 5 (4.7%) | 10 (9.7%) | 14 (13.1%)
Skin And Appendages
Sweating | 15 (14.0%) | 13 (12.6%) | 11 (10.3%)
Abbreviations: COSTART = Coding Symbols for Thesaurus of Adverse Reaction Terms.

The adverse event profile of buprenorphine was also characterized in the dose-controlled study of a buprenorphine ethanolic solution, over a range of doses in four months of treatment. Table 3 shows adverse events reported by at least 5% of subjects in any dose group in the dose-controlled trial.

Table 3. Adverse Events (≥ 5%) by Body System and Treatment Group in a 16 Week Study
Body System/ Adverse Event (COSTART Terminology) | Buprenorphine Dose
Body System/ Adverse Event (COSTART Terminology) | Very Low* N = 184 n (%) | Low* N = 180 n (%) | Moderate* N = 186 n (%) | High* N = 181 n (%) | Total* N = 731 n (%)
Body as a Whole
Abscess | 9 (5%) | 2 (1%) | 3 (2%) | 2 (1%) | 16 (2%)
Asthenia | 26 (14%) | 28 (16%) | 26 (14%) | 24 (13%) | 104 (14%)
Chills | 11 (6%) | 12 (7%) | 9 (5%) | 10 (6%) | 42 (6%)
Fever | 7 (4%) | 2 (1%) | 2 (1%) | 10 (6%) | 21 (3%)
Flu syndrome | 4 (2%) | 13 (7%) | 19 (10%) | 8 (4%) | 44 (6%)
Headache | 51 (28%) | 62 (34%) | 54 (29%) | 53 (29%) | 220 (30%)
Infection | 32 (17%) | 39 (22%) | 38 (20%) | 40 (22%) | 149 (20%)
Injury accidental | 5 (3%) | 10 (6%) | 5 (3%) | 5 (3%) | 25 (3%)
Pain | 47 (26%) | 37 (21%) | 49 (26%) | 44 (24%) | 177 (24%)
Pain back | 18 (10%) | 29 (16%) | 28 (15%) | 27 (15%) | 102 (14%)
Withdrawal syndrome | 45 (24%) | 40 (22%) | 41 (22%) | 36 (20%) | 162 (22%)
Digestive System
Constipation | 10 (5%) | 23 (13%) | 23 (12%) | 26 (14%) | 82 (11%)
Diarrhea | 19 (10%) | 8 (4%) | 9 (5%) | 4 (2%) | 40 (5%)
Dyspepsia | 6 (3%) | 10 (6%) | 4 (2%) | 4 (2%) | 24 (3%)
Nausea | 12 (7%) | 22 (12%) | 23 (12%) | 18 (10%) | 75 (10%)
Vomiting | 8 (4%) | 6 (3%) | 10 (5%) | 14 (8%) | 38 (5%)
Nervous System
Anxiety | 22 (12%) | 24 (13%) | 20 (11%) | 25 (14%) | 91 (12%)
Depression | 24 (13%) | 16 (9%) | 25 (13%) | 18 (10%) | 83 (11%)
Dizziness | 4 (2%) | 9 (5%) | 7 (4%) | 11 (6%) | 31 (4%)
Insomnia | 42 (23%) | 50 (28%) | 43 (23%) | 51 (28%) | 186 (25%)
Nervousness | 12 (7%) | 11 (6%) | 10 (5%) | 13 (7%) | 46 (6%)
Somnolence | 5 (3%) | 13 (7%) | 9 (5%) | 11 (6%) | 38 (5%)
Respiratory System
Cough increase | 5 (3%) | 11 (6%) | 6 (3%) | 4 (2%) | 26 (4%)
Pharyngitis | 6 (3%) | 7 (4%) | 6 (3%) | 9 (5%) | 28 (4%)
Rhinitis | 27 (15%) | 16 (9%) | 15 (8%) | 21 (12%) | 79 (11%)
Skin and Appendages
Sweat | 23 (13%) | 21 (12%) | 20 (11%) | 23 (13%) | 87 (12%)
Special Senses
Runny eyes | 13 (7%) | 9 (5%) | 6 (3%) | 6 (3%) | 34 (5%)
*Sublingual solution. Doses in this table cannot necessarily be delivered in tablet form, but for comparison purposes:
"Very low" dose (1 mg solution) would be less than a tablet dose of 2 mg
"Low" dose (4 mg solution) approximates a 6 mg tablet dose
"Moderate" dose (8 mg solution) approximates a 12 mg tablet dose
"High" dose (16 mg solution) approximates a 24 mg tablet dose

The safety of SUBOXONE sublingual film during treatment induction is supported by a clinical trial using 16 patients treated with SUBOXONE sublingual film and 18 treated with a buprenorphine-only sublingual film. Few differences in the adverse event profiles were noted between SUBOXONE sublingual film and the buprenorphine-only sublingual film.

The most common adverse event occurring during treatment induction and the 3 days following induction using SUBOXONE sublingual film was restlessness. Other adverse events were anxiety, piloerection, stomach discomfort, irritability, headache, rhinorrhea, cold sweat, arthralgia, and lacrimation increased.

Four subjects left the study early on the first day of sublingual film administration. However, there was no evidence to suggest that any of the four subjects experienced precipitated withdrawal secondary to the administration of buprenorphine or buprenorphine/naloxone sublingual films.

6.2 Postmarketing Experience

The following adverse reactions have been identified during post-approval use of SUBOXONE sublingual film. Because these reactions are reported voluntarily from a population of uncertain size, it is not always possible to reliably estimate their frequency or establish a causal relationship to drug exposure.

The most frequently reported postmarketing adverse events were peripheral edema, stomatitis, glossitis, and blistering and ulceration of the mouth or tongue.

Serotonin syndrome: Cases of serotonin syndrome, a potentially life-threatening condition, have been reported during concomitant use of opioids with serotonergic drugs.

Adrenal insufficiency: Cases of adrenal insufficiency have been reported with opioid use, more often following greater than one month of use.

Anaphylaxis: Anaphylaxis has been reported with ingredients contained in SUBOXONE sublingual film.

Androgen deficiency: Cases of androgen deficiency have occurred with chronic use of opioids [see Clinical Pharmacology (12.2)].

Local reactions: Dental decay (including caries, tooth fracture, and tooth loss), glossodynia, glossitis, oral mucosal erythema, oral hypoesthesia, and stomatitis

Hypoglycemia: Cases of hypoglycemia have been reported in patients taking opioids. Most reports were in patients with at least one predisposing risk factor (e.g., diabetes).

Opioid-induced esophageal dysfunction (OIED): Cases of OIED have been reported in patients taking opioids and may occur more frequently in patients taking higher doses of opioids, and/or in patients taking opioids longer term.

7 DRUG INTERACTIONS

Table 4 includes clinically significant drug interactions with SUBOXONE.

Table 4. Clinically Significant Drug Interactions
Benzodiazepines and Other Central Nervous System (CNS) Depressants
Clinical Impact: | Due to additive pharmacologic effects, the concomitant use of benzodiazepines or other CNS depressants, including alcohol, increases the risk of respiratory depression, profound sedation, coma, and death.
Intervention: | Cessation of benzodiazepines or other CNS depressants is preferred in most cases of concomitant use. In some cases, monitoring in a higher level of care for taper may be appropriate. In others, gradually tapering a patient off of a prescribed benzodiazepine or other CNS depressant or decreasing to the lowest effective dose may be appropriate. Before co-prescribing benzodiazepines for anxiety or insomnia, ensure that patients are appropriately diagnosed and consider alternative medications and non-pharmacologic treatments [see Warnings and Precautions (5.2, 5.3)]. If concomitant use is warranted, strongly consider recommending or prescribing an opioid overdose reversal agent, as is recommended for all patients on buprenorphine treatment for opioid use disorder [see Warnings and Precautions (5.2)].
Examples: | Alcohol, benzodiazepines and other sedatives/hypnotics, anxiolytics, tranquilizers, muscle relaxants, general anesthetics, antipsychotics, gabapentinoids (gabapentin or pregabalin), and other opioids.
Inhibitors of CYP3A4
Clinical Impact: | The concomitant use of buprenorphine and CYP3A4 inhibitors can increase the plasma concentration of buprenorphine, resulting in increased or prolonged opioid effects, particularly when an inhibitor is added after a stable dose of SUBOXONE sublingual film is achieved. After stopping a CYP3A4 inhibitor, as the effects of the inhibitor decline, the buprenorphine plasma concentration will decrease [see Clinical Pharmacology (12.3)] , potentially resulting in decreased opioid efficacy or a withdrawal syndrome in patients who had developed physical dependence to buprenorphine.
Intervention: | If concomitant use is necessary, consider dosage reduction of SUBOXONE sublingual film until stable drug effects are achieved. Monitor patients for respiratory depression and sedation at frequent intervals. If a CYP3A4 inhibitor is discontinued, consider increasing the SUBOXONE sublingual film dosage until stable drug effects are achieved. Monitor for signs of opioid withdrawal.
Examples: | Macrolide antibiotics (e.g., erythromycin), azole-antifungal agents (e.g. ketoconazole), protease inhibitors (e.g., ritonavir)
CYP3A4 Inducers
Clinical Impact: | The concomitant use of buprenorphine and CYP3A4 inducers can decrease the plasma concentration of buprenorphine [see Clinical Pharmacology (12.3)] , potentially resulting in decreased efficacy or onset of a withdrawal syndrome in patients who have developed physical dependence to buprenorphine. After stopping a CYP3A4 inducer, as the effects of the inducer decline, the buprenorphine plasma concentration will increase [see Clinical Pharmacology (12.3)] , which could increase or prolong both therapeutic effects and adverse reactions and may cause serious respiratory depression.
Intervention: | If concomitant use is necessary, consider increasing the SUBOXONE sublingual film dosage until stable drug effects are achieved. Monitor for signs of opioid withdrawal. If a CYP3A4 inducer is discontinued, consider SUBOXONE sublingual film dosage reduction and monitor for signs of respiratory depression.
Examples: | Rifampin, carbamazepine, phenytoin
Antiretrovirals: Non-nucleoside reverse transcriptase inhibitors (NNRTIs)
Clinical Impact: | Non-nucleoside reverse transcriptase inhibitors (NNRTIs) are metabolized principally by CYP3A4. Efavirenz, nevirapine, and etravirine are known CYP3A inducers, whereas delavirdine is a CYP3A inhibitor. Significant pharmacokinetic interactions between NNRTIs (e.g., efavirenz and delavirdine) and buprenorphine have been shown in clinical studies, but these pharmacokinetic interactions did not result in any significant pharmacodynamic effects.
Intervention: | Patients who are on chronic SUBOXONE sublingual film treatment should have their dose monitored if NNRTIs are added to their treatment regimen.
Examples: | efavirenz, nevirapine, etravirine, delavirdine
Antiretrovirals: Protease inhibitors (PIs)
Clinical Impact: | Studies have shown some antiretroviral protease inhibitors (PIs) with CYP3A4 inhibitory activity (nelfinavir, lopinavir/ritonavir, ritonavir) have little effect on buprenorphine pharmacokinetic and no significant pharmacodynamic effects. Other PIs with CYP3A4 inhibitory activity (atazanavir and atazanavir/ritonavir) resulted in elevated levels of buprenorphine and norbuprenorphine, and patients in one study reported increased sedation. Symptoms of opioid excess have been found in post-marketing reports of patients receiving buprenorphine and atazanavir with and without ritonavir concomitantly.
Intervention: | Monitor patients taking SUBOXONE sublingual film and atazanavir with and without ritonavir, and reduce dose of SUBOXONE sublingual film if warranted.
Examples: | atazanavir, ritonavir
Antiretrovirals: Nucleoside reverse transcriptase inhibitors (NRTIs)
Clinical Impact: | Nucleoside reverse transcriptase inhibitors (NRTIs) do not appear to induce or inhibit the P450 enzyme pathway, thus no interactions with buprenorphine are expected.
Intervention: | None
Serotonergic Drugs
Clinical Impact: | The concomitant use of opioids with other drugs that affect the serotonergic neurotransmitter system has resulted in serotonin syndrome.
Intervention: | If concomitant use is warranted, carefully observe the patient, particularly during treatment initiation and dose adjustment. Discontinue SUBOXONE sublingual film sublingual film if serotonin syndrome is suspected.
Examples: | Selective serotonin reuptake inhibitors (SSRIs), serotonin and norepinephrine reuptake inhibitors (SNRIs), tricyclic antidepressants (TCAs), triptans, 5-HT3 receptor antagonists, drugs that affect the serotonin neurotransmitter system (e.g., mirtazapine, trazodone, tramadol), certain muscle relaxants (i.e., cyclobenzaprine, metaxalone), monoamine oxidase (MAO) inhibitors
 | (those intended to treat psychiatric disorders and also others, such as linezolid and intravenous methylene blue).
Monoamine Oxidase Inhibitors (MAOIs)
Clinical Impact: | MAOI interactions with opioids may manifest as serotonin syndrome or opioid toxicity (e.g., respiratory depression, coma).
Intervention: | The use of SUBOXONE sublingual film is not recommended for patients taking MAOIs or within 14 days of stopping such treatment.
Examples: | phenelzine, tranylcypromine, linezolid
Muscle Relaxants
Clinical Impact: | Buprenorphine may enhance the neuromuscular blocking action of skeletal muscle relaxants and produce an increased degree of respiratory depression.
Intervention: | Monitor patients receiving muscle relaxants and SUBOXONE sublingual film for signs of respiratory depression that may be greater than otherwise expected and decrease the dosage of SUBOXONE sublingual film and/or the muscle relaxant as necessary. Due to the risk of respiratory depression with concomitant use of skeletal muscle relaxants and opioids, strongly consider recommending or prescribing an opioid overdose reversal agent, as is recommended for all patients on buprenorphine treatment for opioid use disorder [see Dosage and Administration (2.2), Warnings and Precautions (5.2, 5.3)].
Examples: | cyclobenzaprine, metaxalone
Diuretics
Clinical Impact: | Opioids can reduce the efficacy of diuretics by inducing the release of antidiuretic hormone.
Intervention: | Monitor patients for signs of diminished diuresis and/or effects on blood pressure and increase the dosage of the diuretic as needed.
Anticholinergic Drugs
Clinical Impact: | The concomitant use of anticholinergic drugs may increase the risk of urinary retention and/or severe constipation, which may lead to paralytic ileus.
Intervention: | Monitor patients for signs of urinary retention or reduced gastric motility when SUBOXONE sublingual film is used concomitantly with anticholinergic drugs.

8 USE IN SPECIFIC POPULATIONS

8.1 Pregnancy

Risk Summary

The data on use of buprenorphine, one of the active ingredients in SUBOXONE sublingual film, in pregnancy, are limited; however, these data do not indicate an increased risk of major malformations specifically due to buprenorphine exposure. There are limited data from randomized clinical trials in women maintained on buprenorphine that were not designed appropriately to assess the risk of major malformations [see Data]. Observational studies have reported on congenital malformations among buprenorphine-exposed pregnancies, but were also not designed appropriately to assess the risk of congenital malformations specifically due to buprenorphine exposure [see Data]. The extremely limited data on sublingual naloxone exposure in pregnancy are not sufficient to evaluate a drug-associated risk.

Reproductive and developmental studies in rats and rabbits identified adverse events at clinically relevant and higher doses. Embryofetal death was observed in both rats and rabbits administered buprenorphine during the period of organogenesis at doses approximately 6 and 0.3 times, respectively, the human sublingual dose of 16 mg/day of buprenorphine. Pre-and postnatal development studies in rats demonstrated increased neonatal deaths at 0.3 times and above and dystocia at approximately 3 times the human sublingual dose of 16 mg/day of buprenorphine. No clear teratogenic effects were seen when buprenorphine was administered during organogenesis with a range of doses equivalent to or greater than the human sublingual dose of 16 mg/day of buprenorphine. However, increases in skeletal abnormalities were noted in rats and rabbits administered buprenorphine daily during organogenesis at doses approximately 0.6 and approximately equal to the human sublingual dose of 16 mg/day of buprenorphine, respectively. In a few studies, some events such as acephalus and omphalocele were also observed but these findings were not clearly treatment-related [see Data]. Based on animal data, advise pregnant women of the potential risk to a fetus.

The estimated background risk of major birth defects and miscarriage for the indicated population are unknown. All pregnancies have a background risk of birth defect, loss, or other adverse outcomes. In the U.S. general population, the estimated background risk of major birth defects and miscarriage in clinically recognized pregnancies is 2-4% and 15-20%, respectively.

Clinical Considerations

Disease-associated maternal and embryo-fetal risk

Untreated opioid addiction in pregnancy is associated with adverse obstetrical outcomes such as low birth weight, preterm birth, and fetal death. In addition, untreated opioid addiction often results in continued or relapsing illicit opioid use.

Dose Adjustment during Pregnancy and the Postpartum Period

Dosage adjustments of buprenorphine, such as using higher doses, may be required during pregnancy, even if the patient was maintained on a stable dose prior to pregnancy. Dosing should be based on individual response, and withdrawal signs and symptoms should be monitored closely and the dose adjusted as necessary.

Fetal/neonatal adverse reactions

Neonatal opioid withdrawal syndrome may occur in newborn infants of mothers who are receiving treatment with SUBOXONE sublingual film.

Neonatal opioid withdrawal syndrome presents as irritability, hyperactivity and abnormal sleep pattern, high pitched cry, tremor, vomiting, diarrhea, and/or failure to gain weight. Signs of neonatal withdrawal usually occur in the first days after birth. The duration and severity of neonatal opioid withdrawal syndrome may vary. Observe newborns for signs of neonatal opioid withdrawal syndrome and manage accordingly [see Warnings and Precautions (5.5)].

Labor or Delivery

Opioid-dependent women on buprenorphine maintenance therapy may require additional analgesia during labor.

Data

Human Data

Studies have been conducted to evaluate neonatal outcomes in women exposed to buprenorphine during pregnancy. Limited data on malformations from trials, observational studies, case series, and case reports on buprenorphine use in pregnancy do not indicate an increased risk of major malformations specifically due to buprenorphine. Several factors may complicate the interpretation of investigations of the children of women who take buprenorphine during pregnancy, including maternal use of illicit drugs, late presentation for prenatal care, infection, poor compliance, poor nutrition, and psychosocial circumstances. Interpretation of data is complicated further by the lack of information on untreated opioid-dependent pregnant women, who would be the most appropriate group for comparison. Rather, women on another form of opioid medication-assisted treatment, or women in the general population are generally used as the comparison group. However, women in these comparison groups may be different from women prescribed buprenorphine-containing products with respect to maternal factors that may lead to poor pregnancy outcomes.

In a multicenter, double-blind, randomized, controlled trial [Maternal Opioid Treatment: Human Experimental Research (MOTHER)] designed primarily to assess neonatal opioid withdrawal effects, opioid-dependent pregnant women were randomized to buprenorphine (n = 86) or methadone (n = 89) treatment, with enrollment at an average gestational age of 18.7 weeks in both groups. A total of 28 of the 86 women in the buprenorphine group (33%) and 16 of the 89 women in the methadone group (18%) discontinued treatment before the end of pregnancy.

Among women who remained in treatment until delivery, there was no difference between buprenorphine- treated and methadone-treated groups in the number of neonates requiring NOWS treatment or in the peak severity of NOWS. Buprenorphine-exposed neonates required less morphine (mean total dose, 1.1 mg vs. 10.4 mg), had shorter hospital stays (10.0 days vs. 17.5 days), and shorter duration of treatment for NOWS (4.1 days vs. 9.9 days) compared to the methadone-exposed group. There were no differences between groups in other primary outcomes (neonatal head circumference,) or secondary outcomes (weight and length at birth, preterm birth, gestational age at delivery, and 1-minute and 5-minute Apgar scores), or in the rates of maternal or neonatal adverse events. The outcomes among mothers who discontinued treatment before delivery and may have relapsed to illicit opioid use are not known. Because of the imbalance in discontinuation rates between the buprenorphine and methadone groups, the study findings are difficult to interpret.

Animal Data

The exposure margins listed below are based on body surface area comparisons (mg/m^2) to the human sublingual dose of 16 mg buprenorphine via SUBOXONE sublingual tablets.

Effects on embryo-fetal development were studied in Sprague-Dawley rats and Russian white rabbits following oral (1:1) and intramuscular (IM) (3:2) administration of mixtures of buprenorphine and naloxone during the period of organogenesis. Following oral administration to rats no teratogenic effects were observed at buprenorphine doses up to 250 mg/kg/day (estimated exposure approximately 150 times the human sublingual dose of 16 mg) in the presence of maternal toxicity (mortality). Following oral administration to rabbits, no teratogenic effects were observed at buprenorphine doses up to 40 mg/kg/day (estimated exposure approximately 50 times, the human sublingual dose of 16 mg) in the absence of clear maternal toxicity.

No definitive drug-related teratogenic effects were observed in rats and rabbits at IM doses up to 30 mg/kg/day (estimated exposure approximately 20 times and 35 times, respectively, the human sublingual dose of 16 mg). Maternal toxicity resulting in mortality was noted in these studies in both rats and rabbits.

Acephalus was observed in one rabbit fetus from the low-dose group and omphalocele was observed in two rabbit fetuses from the same litter in the mid-dose group; no findings were observed in fetuses from the high-dose group. Maternal toxicity was seen in the high-dose group but not at the lower doses where the findings were observed. Following oral administration of buprenorphine to rats, dose-related post-implantation losses, evidenced by increases in the numbers of early resorptions with consequent reductions in the numbers of fetuses, were observed at doses of 10 mg/kg/day or greater (estimated exposure approximately 6 times the human sublingual dose of 16 mg). In the rabbit, increased post-implantation losses occurred at an oral dose of 40 mg/kg/day. Following IM administration in the rat and the rabbit, post-implantation losses, as evidenced by decreases in live fetuses and increases in resorptions, occurred at 30 mg/kg/day.

Buprenorphine was not teratogenic in rats or rabbits after IM or subcutaneous (SC) doses up to 5 mg/kg/day (estimated exposure was approximately 3 and 6 times, respectively, the human sublingual dose of 16 mg), after IV doses up to 0.8 mg/kg/day (estimated exposure was approximately 0.5 times and equal to, respectively, the human sublingual dose of 16 mg), or after oral doses up to 160 mg/kg/day in rats (estimated exposure was approximately 95 times the human sublingual dose of 16 mg) and 25 mg/kg/day in rabbits (estimated exposure was approximately 30 times the human daily sublingual dose of 16 mg). Significant increases in skeletal abnormalities (e.g., extra thoracic vertebra or thoraco-lumbar ribs) were noted in rats after SC administration of 1 mg/kg/day and up (estimated exposure was approximately 0.6 times the human sublingual dose of 16 mg), but were not observed at oral doses up to 160 mg/kg/day. Increases in skeletal abnormalities in rabbits after IM administration of 5 mg/kg/day (estimated exposure was approximately 6 times the human daily sublingual dose of 16 mg) in the absence of maternal toxicity or oral administration of 1 mg/kg/day or greater (estimated exposure was approximately equal to the human sublingual dose of 16 mg) were not statistically significant.

In rabbits, buprenorphine produced statistically significant pre-implantation losses at oral doses of 1 mg/kg/day or greater and post-implantation losses that were statistically significant at IV doses of 0.2 mg/kg/day or greater (estimated exposure approximately 0.3 times the human daily sublingual dose of 16 mg). No maternal toxicity was noted at doses causing post-implantation loss in this study.

Dystocia was noted in pregnant rats treated intramuscularly with buprenorphine from Gestation Day 14 through Lactation Day 21 at 5 mg/kg/day (approximately 3 times the human sublingual dose of 16 mg). Fertility, pre- and post-natal development studies with buprenorphine in rats indicated increases in neonatal mortality after oral doses of 0.8 mg/kg/day and up (approximately 0.5 times the human daily sublingual dose of 16 mg), after IM doses of 0.5 mg/kg/day and up (approximately 0.3 times the human sublingual dose of 16 mg), and after SC doses of 0.1 mg/kg/day and up (approximately 0.06 times the human sublingual dose of 16 mg).

An apparent lack of milk production during these studies likely contributed to the decreased pup viability and lactation indices.

Delays in the occurrence of righting reflex and startle response were noted in rat pups at an oral dose of 80 mg/kg/day (approximately 50 times the human sublingual dose of 16 mg).

8.2 Lactation

Risk Summary

Based on two studies in 13 lactating women maintained on buprenorphine treatment, buprenorphine and its metabolite norbuprenorphine were present in low levels in human milk and infant urine.

Available data have not shown adverse reactions in breastfed infants. There are no data on the combination product buprenorphine/naloxone in breastfeeding, however oral absorption of naloxone is limited. The developmental and health benefits of breastfeeding should be considered along with the mother's clinical need for SUBOXONE sublingual film and any potential adverse effects on the breastfed child from the drug or from the underlying maternal condition.

Clinical Considerations

Advise breastfeeding women taking buprenorphine products to monitor the infant for increased drowsiness and breathing difficulties.

Data

Data were consistent from two studies (N = 13) of breastfeeding infants whose mothers were maintained on sublingual doses of buprenorphine ranging from 2.4 to 24 mg/day, showing that the infants were exposed to less than 1% of the maternal daily dose.

In a study of six lactating women who were taking a median sublingual buprenorphine dose of 0.29 mg/kg/day 5 to 8 days after delivery, breast milk provided a median infant dose of 0.42 mcg/kg/day of buprenorphine and 0.33 mcg/kg/day of norbuprenorphine, equal to 0.2% and 0.12%, respectively, of the maternal weight-adjusted dose (relative dose/kg (%) of norbuprenorphine was calculated from the assumption that buprenorphine and norbuprenorphine are equipotent).

Data from a study of seven lactating women who were taking a median sublingual buprenorphine dose of 7 mg/day an average of 1.12 months after delivery indicated that the mean milk concentrations (Cavg) of buprenorphine and norbuprenorphine were 3.65 mcg/L and 1.94 mcg/L respectively. Based on the study data, and assuming milk consumption of 150 mL/kg/day, an exclusively breastfed infant would receive an estimated mean absolute infant dose (AID) of 0.55 mcg/kg/day of buprenorphine and 0.29 mcg/kg/day of norbuprenorphine, or a mean relative infant dose (RID) of 0.38% and 0.18%, respectively, of the maternal weight-adjusted dose.

8.3 Females and Males of Reproductive Potential

Infertility

Chronic use of opioids may cause reduced fertility in females and males of reproductive potential. It is not known whether these effects on fertility are reversible [see Adverse Reactions (6.2), Clinical Pharmacology (12.2), Nonclinical Toxicology (13.1)].

8.4 Pediatric Use

The safety and effectiveness of SUBOXONE sublingual film have not been established in pediatric patients. This product is not appropriate for the treatment of neonatal abstinence syndrome in neonates, because it contains naloxone, an opioid antagonist.

8.5 Geriatric Use

Clinical studies of SUBOXONE sublingual film, SUBOXONE sublingual tablets, or SUBUTEX sublingual tablets did not include sufficient numbers of subjects aged 65 and over to determine whether they responded differently than younger subjects. Other reported clinical experience has not identified differences in responses between the elderly and younger patients. Due to possible decreased hepatic, renal, or cardiac function and of concomitant disease or other drug therapy in geriatric patients, the decision to prescribe SUBOXONE sublingual film should be made cautiously in individuals 65 years of age or older and these patients should be monitored for signs and symptoms of toxicity or overdose.

8.6 Hepatic Impairment

The effect of hepatic impairment on the pharmacokinetics of buprenorphine and naloxone has been evaluated in a pharmacokinetic study. Both drugs are extensively metabolized in the liver. While no clinically significant changes have been observed in subjects with mild hepatic impairment; the plasma levels have been shown to be higher and half-life values have been shown to be longer for both buprenorphine and naloxone in subjects with moderate and severe hepatic impairment. The magnitude of the effects on naloxone are greater than that on buprenorphine in both moderately and severely impaired subjects. The difference in magnitude of the effects on naloxone and buprenorphine are greater in subjects with severe hepatic impairment than in subjects with moderate hepatic impairment, and therefore the clinical impact of these effects is likely to be greater in patients with severe hepatic impairment than in patients with moderate hepatic impairment.

Buprenorphine/naloxone products should be avoided in patients with severe hepatic impairment and may not be appropriate for patients with moderate hepatic impairment [see Warnings and Precautions (5.12), Clinical Pharmacology (12.3)].

8.7 Renal Impairment

No differences in buprenorphine pharmacokinetics were observed between 9 dialysis-dependent and 6 normal patients following IV administration of 0.3 mg buprenorphine. The effects of renal failure on naloxone pharmacokinetics are unknown.

9 DRUG ABUSE AND DEPENDENCE

9.1 Controlled Substance

SUBOXONE sublingual film contains buprenorphine, a Schedule III controlled substance under the Controlled Substances Act.

9.2 Abuse

Buprenorphine, like morphine and other opioids, has the potential for being abused and is subject to criminal diversion. This should be considered when prescribing or dispensing buprenorphine in situations when the clinician is concerned about an increased risk of misuse, abuse, or diversion. Healthcare professionals should contact their state professional licensing board or state controlled substances authority for information on how to prevent and detect abuse or diversion of this product.

Patients who continue to misuse, abuse, or divert buprenorphine products or other opioids should be provided with or referred for more intensive and structured treatment.

Abuse of buprenorphine poses a risk of overdose and death. This risk is increased with the abuse of buprenorphine and alcohol and other substances, especially benzodiazepines.

The healthcare provider may be able to more easily detect misuse or diversion by maintaining records of medication prescribed including date, dose, quantity, frequency of refills, and renewal requests of medication prescribed.

Proper assessment of the patient, proper prescribing practices, periodic re-evaluation of therapy, and proper handling and storage of the medication are appropriate measures that help to limit abuse of opioid drugs.

9.3 Dependence

Buprenorphine is a partial agonist at the mu-opioid receptor and chronic administration produces physical dependence of the opioid type, characterized by moderate withdrawal signs and symptoms upon abrupt discontinuation or rapid taper. The withdrawal syndrome is typically milder than seen with full agonists and may be delayed in onset [see Warnings and Precautions (5.7)].

Neonatal opioid withdrawal syndrome (NOWS) is an expected and treatable outcome of prolonged use of opioids during pregnancy [see Warnings and Precautions (5.5)].

10 OVERDOSAGE

Clinical Presentation

The manifestations of acute buprenorphine overdose include pinpoint pupils, sedation, hypotension, hypoglycemia, respiratory depression, and death.

Toxic leukoencephalopathy has been reported after opioid overdose and can present hours, days, or weeks after apparent recovery from the initial intoxication.

Treatment of Overdose

In the event of overdose, the respiratory and cardiac status of the patient should be monitored carefully. When respiratory or cardiac functions are depressed, primary attention should be given to the re-establishment of adequate respiratory exchange through provision of a patent airway and institution of assisted or controlled ventilation. Oxygen, IV fluids, vasopressors, and other supportive measures should be employed as indicated.

In the case of overdose, the primary management should be the re-establishment of adequate ventilation with mechanical assistance of respiration, if required. An opioid overdose reversal agent may be of value for the management of buprenorphine overdose. Higher than normal doses and repeated administration may be necessary. The long duration of action of SUBOXONE sublingual film should be taken into consideration when determining the length of treatment and medical surveillance needed to reverse the effects of an overdose. Insufficient duration of monitoring may put patients at risk.

11 DESCRIPTION

SUBOXONE® (buprenorphine and naloxone) sublingual film is an orange film, imprinted with a logo identifying the product and strength in white ink. It contains buprenorphine HCl, a mu-opioid receptor partial agonist, and a kappa-opioid receptor antagonist, and naloxone HCl dihydrate, an opioid antagonist, at a ratio of 4:1 (ratio of free bases). It is intended for sublingual or buccal administration and is available in four dosage strengths, 2 mg buprenorphine with 0.5 mg naloxone, 4 mg buprenorphine with 1 mg naloxone, 8 mg buprenorphine with 2 mg naloxone and 12 mg buprenorphine with 3 mg naloxone. Each film also contains polyethylene oxide, hydroxypropyl methylcellulose, maltitol, acesulfame potassium, lime flavor, citric acid, sodium citrate, FD&C yellow #6, and white ink.

Chemically, buprenorphine HCl is (2S)-2-[17-Cyclopropylmethyl-4,5α-epoxy-3-hydroxy-6-methoxy-6α,14- ethano-14α-morphinan-7α-yl]-3,3-dimethylbutan-2-ol hydrochloride. It has the following chemical structure:

Buprenorphine HCl has the molecular formula C29H41NO4• HCl and the molecular weight is 504.10. It is a white or off-white crystalline powder, sparingly soluble in water, freely soluble in methanol, soluble in alcohol, and practically insoluble in cyclohexane.

Chemically, naloxone HCl dihydrate is 17-Allyl-4,5 α -epoxy-3, 14-dihydroxymorphinan-6-one hydrochloride dihydrate. It has the following chemical structure:

Naloxone hydrochloride dihydrate has the molecular formula C19H21NO4• HCl • 2H2O and the molecular weight is 399.87. It is a white to slightly off-white powder and is freely soluble in water, soluble in alcohol, and practically insoluble in toluene and ether.

12 CLINICAL PHARMACOLOGY

12.1 Mechanism of Action

SUBOXONE sublingual film contains buprenorphine and naloxone. Buprenorphine is a partial agonist at the mu-opioid receptor and an antagonist at the kappa-opioid receptor. Naloxone is a potent antagonist at mu opioid receptors and produces opioid withdrawal signs and symptoms in individuals physically dependent on full opioid agonists when administered parenterally.

12.2 Pharmacodynamics

Subjective Effects

Comparisons of buprenorphine to full opioid agonists such as methadone and hydromorphone suggest that sublingual buprenorphine produces typical opioid agonist effects which are limited by a ceiling effect.

In opioid-experienced subjects who were not physically dependent, acute sublingual doses of buprenorphine/naloxone tablets produced opioid agonist effects which reached a maximum between doses of 8 mg/2 mg and 16 mg/4 mg buprenorphine/naloxone.

Opioid agonist ceiling-effects were also observed in a double-blind, parallel group, dose-ranging comparison of single doses of buprenorphine sublingual solution (1, 2, 4, 8, 16, or 32 mg), placebo and a full agonist control at various doses. The treatments were given in ascending dose order at intervals of at least one week to 16 opioid-experienced subjects who were not physically dependent. Both active drugs produced typical opioid agonist effects. For all measures for which the drugs produced an effect, buprenorphine produced a dose- related response. However, in each case, there was a dose that produced no further effect. In contrast, the highest dose of the full agonist control always produced the greatest effects. Agonist objective rating scores remained elevated for the higher doses of buprenorphine (8 mg to 32 mg) longer than for the lower doses and did not return to baseline until 48 hours after drug administration. The onset of effects appeared more rapidly with buprenorphine than with the full agonist control, with most doses nearing peak effect after 100 minutes for buprenorphine compared to 150 minutes for the full agonist control.

Physiologic Effects

Buprenorphine in IV (2, 4, 8, 12 and 16 mg) and sublingual (12 mg) doses has been administered to opioid- experienced subjects who were not physically dependent to examine cardiovascular, respiratory, and subjective effects at doses comparable to those used for treatment of opioid dependence. Compared to placebo, there were no statistically significant differences among any of the treatment conditions for blood pressure, heart rate, respiratory rate, O2 saturation, or skin temperature across time. Systolic BP was higher in the 8 mg group than placebo (3 hour AUC values). Minimum and maximum effects were similar across all treatments. Subjects remained responsive to low voice and responded to computer prompts. Some subjects showed irritability, but no other changes were observed. The respiratory effects of sublingual buprenorphine were compared with the effects of methadone in a double- blind, parallel group, dose ranging comparison of single doses of buprenorphine sublingual solution (1, 2, 4, 8, 16, or 32 mg) and oral methadone (15, 30, 45, or 60 mg) in non-dependent, opioid-experienced volunteers. In this study, hypoventilation not requiring medical intervention was reported more frequently after buprenorphine doses of 4 mg and higher than after methadone. Both drugs decreased O2 saturation to the same degree.

Effect of Naloxone

Physiologic and subjective effects following acute sublingual administration of buprenorphine tablets and buprenorphine/naloxone tablets were similar at equivalent dose levels of buprenorphine. Naloxone had no clinically significant effect when administered by the sublingual route, although blood levels of the drug were measurable. Buprenorphine/naloxone, when administered sublingually to an opioid-dependent cohort, was recognized as an opioid agonist, whereas when administered intramuscularly, combinations of buprenorphine with naloxone produced opioid antagonist actions similar to naloxone. This finding suggests that the naloxone in buprenorphine/naloxone tablets may deter injection of buprenorphine/naloxone tablets by persons with active substantial heroin or other full mu-opioid dependence. However, clinicians should be aware that some opioid-dependent persons, particularly those with a low level of full mu-opioid physical dependence or those whose opioid physical dependence is predominantly to buprenorphine, abuse buprenorphine/naloxone combinations by the intravenous or intranasal route. In methadone-maintained patients and heroin- dependent subjects, IV administration of buprenorphine/naloxone combinations precipitated opioid withdrawal signs and symptoms and was perceived as unpleasant and dysphoric. In morphine-stabilized subjects, intravenously administered combinations of buprenorphine with naloxone produced opioid antagonist and withdrawal signs and symptoms that were ratio-dependent; the most intense withdrawal signs and symptoms were produced by 2:1 and 4:1 ratios, less intense by an 8:1 ratio.

Effects on the Endocrine System

Opioids inhibit the secretion of adrenocorticotropic hormone (ACTH), cortisol, and luteinizing hormone (LH) in humans [see Adverse Reactions (6.2)]. They also stimulate prolactin, growth hormone (GH) secretion, and pancreatic secretion of insulin and glucagon.

Chronic use of opioids may influence the hypothalamic-pituitary-gonadal axis, leading to androgen deficiency that may manifest as low libido, impotence, erectile dysfunction, amenorrhea, or infertility. The causal role of opioids in the clinical syndrome of hypogonadism is unknown because the various medical, physical, lifestyle, and psychological stressors that may influence gonadal hormone levels have not been adequately controlled for in studies conducted to date. Patients presenting with symptoms of androgen deficiency should undergo laboratory evaluation.

Cardiac Electrophysiology

Thorough QT studies with buprenorphine products have demonstrated QT prolongation ≤ 15 msec.

12.3 Pharmacokinetics

Absorption

In several pharmacokinetic studies following the administration of different dosages, a dose of one or two of the 2 mg/0.5 mg SUBOXONE sublingual films administered sublingually or buccally showed comparable relative bioavailability to the same total dose of SUBOXONE sublingual tablets. In contrast, one 8 mg/2 mg and one 12 mg/3 mg SUBOXONE sublingual films administered sublingually or buccally showed higher relative bioavailability for both buprenorphine and naloxone compared to the same total dose of SUBOXONE sublingual tablets. A combination of one 8 mg/2 mg and two 2 mg/0.5 mg SUBOXONE sublingual films (total dose of 12 mg/3 mg) administered sublingually showed comparable relative bioavailability to the same total dose of SUBOXONE sublingual tablets, while buccally administered SUBOXONE sublingual films showed higher relative bioavailability. Table 5, below, illustrates the relative increase in exposure to buprenorphine and naloxone associated with SUBOXONE sublingual films compared to SUBOXONE sublingual tablets, and shows the effect of route of administration [see Dosage and Administration (2.9, 2.10)].

Across relevant pharmacokinetic studies, the pharmacokinetic parameters and exposures derived from the buccal and sublingual administrations of SUBOXONE sublingual film were comparable to one another.

Table 5. Changes in Pharmacokinetic Parameters for SUBOXONE Sublingual Film Administered Sublingually or Buccally in Comparison to SUBOXONE Sublingual Tablet
Dosage | PK Parameter | Increase in Buprenorphine |  |  | PK Parameter | Increase in Naloxone
Dosage | PK Parameter | Film Sublingual Compared to Tablet Sublingual | Film Buccal Compared to Tablet Sublingual | Film Buccal Compared to Film Sublingual | PK Parameter | Film Sublingual Compared to Tablet Sublingual | Film Buccal Compared to Tablet Sublingual | Film Buccal Compared to Film Sublingual
1 x 2 mg/0.5 mg | Cmax | 22% | 25% | - | Cmax | - | - | -
1 x 2 mg/0.5 mg | AUC0-last | - | 19% | - | AUC0-last | - | - | -
2 x 2 mg/0.5 mg | Cmax | - | 21% | 21% | Cmax | - | 17% | 21%
2 x 2 mg/0.5 mg | AUC0-last | - | 23% | 16% | AUC0-last | - | 22% | 24%
1 x 8 mg/2 mg | Cmax | 28% | 34% | - | Cmax | 41% | 54% | -
1 x 8 mg/2 mg | AUC0-last | 20% | 25% | - | AUC0-last | 30% | 43% | -
1 x 12 mg/3 mg | Cmax | 37% | 47% | - | Cmax | 57% | 72% | 9%
1 x 12 mg/3 mg | AUC0-last | 21% | 29% | - | AUC0-last | 45% | 57% | -
1 x 8 mg/2 mg plus 2 x 2 mg/0.5 mg | Cmax | - | 27% | 13% | Cmax | 17% | 38% | 19%
1 x 8 mg/2 mg plus 2 x 2 mg/0.5 mg | AUC0-last | - | 23% | - | AUC0-last | - | 30% | 19%
1 x 16 mg/4 mg film | Cmax | 34% | 29% | 7% | Cmax | 44% | 46% | 9%
1 x 16 mg/4 mg film | AUC0-last | 32% | - | - | AUC0-last | 49% | 36% | 3%
Note: 1. the 16 mg/4 mg strength film is not marketed; it is compositionally proportional to the 8 mg/2 mg strength film and has the same size of 2 x 8 mg/2 mg film. 2. – represents no change when the 90% confidence intervals for the geometric mean ratios of the Cmax and AUC0-last values are within the 80% to 125% limit. 3. There are no data for the 4 mg/1 mg strength film; it is compositionally proportional to 2 mg/0.5 mg strength film and has the same size of 2 x 2 mg/0.5 mg film strength.

Distribution

Buprenorphine is approximately 96% protein bound, primarily to alpha and beta globulin. Naloxone is approximately 45% protein bound, primarily to albumin.

Elimination

Buprenorphine is metabolized and eliminated in urine and feces. Naloxone undergoes metabolism as well. When SUBOXONE sublingual film is administered sublingually or buccally, buprenorphine has a mean elimination half-life ranging from 24 to 42 hours and naloxone has a mean elimination half-life ranging from 2 to 12 hours.

Metabolism

Buprenorphine undergoes both N-dealkylation to norbuprenorphine and glucuronidation. The N-dealkylation pathway is mediated primarily by the CYP3A4. Norbuprenorphine, the major metabolite, can further undergo glucuronidation. Norbuprenorphine has been found to bind opioid receptors in vitro; however, it has not been studied clinically for opioid-like activity. Naloxone undergoes direct glucuronidation to naloxone-3-glucuronide as well as N-dealkylation, and reduction of the 6-oxo group.

Excretion

A mass balance study of buprenorphine showed complete recovery of radiolabel in urine (30%) and feces (69%) collected up to 11 days after dosing. Almost all of the dose was accounted for in terms of buprenorphine, norbuprenorphine, and two unidentified buprenorphine metabolites. In urine, most of buprenorphine and norbuprenorphine was conjugated (buprenorphine, 1% free and 9.4% conjugated; norbuprenorphine, 2.7% free and 11% conjugated). In feces, almost all of the buprenorphine and norbuprenorphine were free (buprenorphine, 33% free and 5% conjugated; norbuprenorphine, 21% free and 2% conjugated). Based on all studies performed with sublingually and buccally administered SUBOXONE sublingual film, buprenorphine has a mean elimination half-life from plasma ranging from 24 to 42 hours and naloxone has a mean elimination half-life from plasma ranging from 2 to 12 hours.

Drug Interactions Studies

CYP3A4 Inhibitors and Inducers

Buprenorphine has been found to be a CYP2D6 and CYP3A4 inhibitor and its major metabolite, norbuprenorphine, has been found to be a moderate CYP2D6 inhibitor in in vitro studies employing human liver microsomes. However, the relatively low plasma concentrations of buprenorphine and norbuprenorphine resulting from therapeutic doses are not expected to raise significant drug-drug interaction concerns [see Drug Interactions (7)].

Specific Populations

Hepatic Impairment

In a pharmacokinetic study, the disposition of buprenorphine and naloxone were determined after administering a 2.0/0.5 mg SUBOXONE sublingual tablet in subjects with varied degrees of hepatic impairment as indicated by Child-Pugh criteria. The disposition of buprenorphine and naloxone in patients with hepatic impairment were compared to disposition in subjects with normal hepatic function.

In subjects with mild hepatic impairment, the changes in mean Cmax, AUC0-last, and half-life values of both buprenorphine and naloxone were not clinically significant. No dosing adjustment is needed in patients with mild hepatic impairment.

For subjects with moderate and severe hepatic impairment, mean Cmax, AUC0-last, and half-life values of both buprenorphine and naloxone were increased; the effects on naloxone are greater than that on buprenorphine (Table 6).

Table 6. Changes in Pharmacokinetic Parameters in Subjects With Moderate and Severe Hepatic Impairment
Hepatic Impairment | PK Parameters | Increase in buprenorphine compared to healthy subjects | Increase in naloxone compared to healthy subjects
Moderate | Cmax | 8% | 170%
Moderate | AUC0-last | 64% | 218%
Moderate | Half-life | 35% | 165%
Severe | Cmax | 72% | 1030%
Severe | AUC0-last | 181% | 1302%
Severe | Half-life | 57% | 122%

The difference in magnitude of the effects on naloxone and buprenorphine are greater in subjects with severe hepatic impairment than subjects with moderate hepatic impairment [see Warnings and Precautions (5.12), Use in Specific Populations (8.6)].

HCV infection

In subjects with HCV infection but no sign of hepatic impairment, the changes in the mean Cmax, AUC0-last, and half-life values of buprenorphine and naloxone were not clinically significant in comparison to healthy subjects without HCV infection.

13 NONCLINICAL TOXICOLOGY

13.1 Carcinogenesis, Mutagenesis, Impairment of Fertility

Carcinogenicity

Carcinogenicity data on SUBOXONE sublingual film are not available.

A carcinogenicity study of buprenorphine/naloxone (4:1 ratio of the free bases) was performed in Alderley Park rats. Buprenorphine/naloxone was administered in the diet at doses of approximately 7, 31, and 123 mg/kg/day for 104 weeks (estimated exposure was approximately 4, 18, and 44 times the recommended human sublingual dose of 16 mg/4 mg buprenorphine/naloxone based on buprenorphine AUC comparisons). A statistically significant increase in Leydig cell adenomas was observed in all dose groups. No other drug-related tumors were noted.

Carcinogenicity studies of buprenorphine were conducted in Sprague-Dawley rats and CD-1 mice. Buprenorphine was administered in the diet to rats at doses of 0.6, 5.5, and 56 mg/kg/day (estimated exposure was approximately 0.4, 3, and 35 times the recommended human daily sublingual dose of 16 mg on a mg/m^2 basis) for 27 months. As in the buprenorphine/naloxone carcinogenicity study in rats, statistically significant dose-related increases in Leydig cell tumors occurred. In an 86 week study in CD-1 mice, buprenorphine was not carcinogenic at dietary doses up to 100 mg/kg/day (estimated exposure was approximately 30 times the recommended human daily sublingual dose of 16 mg on a mg/m^2 basis).

Mutagenicity

The 4:1 combination of buprenorphine and naloxone was not mutagenic in a bacterial mutation assay (Ames test) using four strains of S. typhimurium and two strains of E. coli. The combination was not clastogenic in an in vitro cytogenetic assay in human lymphocytes or in an IV micronucleus test in the rat.

Buprenorphine was studied in a series of tests utilizing gene, chromosome, and DNA interactions in both prokaryotic and eukaryotic systems. Results were negative in yeast (S. cerevisiae) for recombinant, gene convertant, or forward mutations; negative in Bacillus subtilis “rec” assay, negative for clastogenicity in CHO cells, Chinese hamster bone marrow and spermatogonia cells, and negative in the mouse lymphoma L5178Y assay.

Results were equivocal in the Ames test: negative in studies in two laboratories, but positive for frame shift mutation at a high dose (5 mg/plate) in a third study. Results were positive in the Green-Tweets (E. coli) survival test, positive in a DNA synthesis inhibition (DSI) test with testicular tissue from mice, for both in vivo and in vitro incorporation of [^3H]thymidine, and positive in unscheduled DNA synthesis (UDS) test using testicular cells from mice.

Impairment of Fertility

Dietary administration of buprenorphine in the rat at dose levels of 500 ppm or greater (equivalent to approximately 47 mg/kg/day or greater; estimated exposure approximately 28 times the recommended human daily sublingual dose of 16 mg on a mg/m^2 basis) produced a reduction in fertility demonstrated by reduced female conception rates. A dietary dose of 100 ppm (equivalent to approximately 10 mg/kg/day; estimated exposure approximately 6 times the recommended human daily sublingual dose of 16 mg on a mg/m^2 basis) had no adverse effect on fertility.

16 HOW SUPPLIED / STORAGE AND HANDLING

SUBOXONE sublingual film is supplied as an orange rectangular film with a white printed logo in child-resistant polyester/foil laminated pouches:

- NDC 12496-1202-3 (buprenorphine 2 mg/naloxone 0.5 mg/film; content expressed in terms of free base, equivalent to 2.16 mg buprenorphine hydrochloride USP and 0.61 mg naloxone hydrochloride dihydrate USP) - 30 films per carton
- NDC 12496-1204-3 (buprenorphine 4 mg/naloxone 1 mg/film; content expressed in terms of free base, equivalent to 4.32 mg buprenorphine hydrochloride USP and 1.22 mg naloxone hydrochloride dihydrate USP) - 30 films per carton
- NDC 12496-1208-3 (buprenorphine 8 mg/naloxone 2 mg/film; content expressed in terms of free base, equivalent to 8.64 mg buprenorphine hydrochloride USP and 2.44 mg naloxone hydrochloride dihydrate USP) - 30 films per carton
- NDC 12496-1212-3 (buprenorphine 12 mg/naloxone 3 mg/film; content expressed in terms of free base, equivalent to 12.96 mg buprenorphine hydrochloride USP and 3.66 mg naloxone hydrochloride dihydrate USP) - 30 films per carton

Store at 25°C (77°F), excursions permitted to 15-30°C (59-86°F) [see USP Controlled Room Temperature].

Store SUBOXONE sublingual film securely and dispose of properly [see Patient Counseling Information (17)].

17 PATIENT COUNSELING INFORMATION

Advise patients to read the FDA-approved patient labeling (Medication Guide).

Storage and Disposal

Because of the risks associated with accidental ingestion, misuse, and abuse, advise patients to store SUBOXONE sublingual film securely, out of sight and reach of children, and in a location not accessible by others, including visitors to the home [see Warnings and Precautions (5.1, 5.4), Drug Abuse and Dependence (9.2)]. Inform patients that leaving SUBOXONE sublingual film unsecured can pose a deadly risk to others in the home.

Advise patients and caregivers that when medicines are no longer needed, they should be disposed of promptly. Expired, unwanted, or unused SUBOXONE sublingual film should be disposed of by removing the SUBOXONE sublingual film from the foil packaging, and flushing the unused medication down the toilet (if a drug take-back option is not readily available). Inform patients that they can visit www.fda.gov/drugdisposal for a complete list of medicines recommended for disposal by flushing, as well as additional information on disposal of unused medicines.

Safe Use

Before initiating treatment with SUBOXONE sublingual film, explain the points listed below to caregivers and patients. Instruct patients to read the Medication Guide each time SUBOXONE sublingual film is dispensed because new information may be available.

- SUBOXONE sublingual film must be administered whole. Advise patients not to cut, chew, or swallow SUBOXONE sublingual film.
- Inform patients and caregivers that potentially fatal additive effects may occur if SUBOXONE sublingual film is used with benzodiazepines or other CNS depressants (e.g., alcohol, non-benzodiazepine sedative/hypnotics, anxiolytics, tranquilizers, muscle relaxants, general anesthetics, antipsychotics, gabapentinoids [gabapentin or pregabalin], and other opioids) and not to use these concomitantly unless supervised by a healthcare provider [see Warnings and Precautions (5.2, 5.3), Drug Interactions (7)].
- Educate patients and caregivers on how to recognize respiratory depression and emphasize the importance of calling 911 or getting emergency medical help right away in the event of a known or suspected overdose [see Warnings and Precautions (5.2)].
- Patient Access to an Opioid Overdose Reversal Agent for the Emergency Treatment of Opioid Overdose
  Inform patients and caregivers about opioid overdose reversal agents (e.g., naloxone, nalmefene) and discuss the importance of having access to an opioid overdose reversal agent. Because patients being treated for opioid use disorder are at risk for relapse, discuss the importance of having access to an opioid overdose reversal agent. Also discuss the importance of having access to an opioid overdose reversal agent if there are household members (including children) or other close contacts at risk for accidental ingestion or opioid overdose.
  Discuss with the patient the options for obtaining an opioid overdose reversal agent (e.g., prescription, over-the-counter (some products), or as part of a community-based program) [see Dosage and Administration (2.2), Warnings and Precautions (5.2)].
  There are important differences among the opioid overdose reversal agents. Be familiar with these differences, as outlined in the approved labeling for those products, prior to recommending or prescribing such an agent.
  Educate patients and caregivers on how to recognize the signs and symptoms of an opioid overdose.
  Explain to patients and caregivers that effects of opioid overdose reversal agents like naloxone and nalmefene are temporary, and that they must call 911 or get emergency medical help right away in all cases of known or suspected opioid overdose, even if an opioid overdose reversal agent is administered. Repeat administration may be necessary, particularly for overdose involving buprenorphine [see Dosage and Administration (2.2), Warnings and Precautions (5.2), Overdosage (10)].
  Advise patients and caregivers:
  - how to treat with an opioid overdose reversal agent in the event of an opioid overdose.
  - to tell family and friends about their opioid overdose reversal agent, and to keep it in a place where family and friends can easily access it in an emergency.
  - to read the Patient Information (or other educational material) that will come with their opioid overdose reversal agent. Emphasize the importance of doing this before an opioid emergency happens, so the patient and caregiver will know what to do.
- Advise patients that SUBOXONE sublingual film contains an opioid that can be a target for people who abuse prescription medications or street drugs. Caution patients to keep their films in a safe place, and to protect them from theft.
- Instruct patients to keep SUBOXONE sublingual film in a secure place, out of the sight and reach of children. Accidental or deliberate ingestion by a child may cause respiratory depression that can result in death. Advise patients to seek medical attention immediately if a child is exposed to SUBOXONE sublingual film.
- Inform patients that opioids could cause a rare but potentially life-threatening condition resulting from concomitant administration of serotonergic drugs. Warn patients of the symptoms of serotonin syndrome and to seek medical attention right away if symptoms develop. Instruct patients to inform their healthcare providers if they are taking, or plan to take serotonergic medications [see Drug Interactions (7)].
- Inform patients that opioids could cause adrenal insufficiency, a potentially life- threatening condition. Adrenal insufficiency may present with non-specific symptoms and signs such as nausea, vomiting, anorexia, fatigue, weakness, dizziness, and low blood pressure. Advise patients to seek medical attention if they experience a constellation of these symptoms [see Warnings and Precautions (5.6)].
- Advise patients to never give SUBOXONE sublingual film to anyone else, even if he or she has the same signs and symptoms. It may cause harm or death.
- Advise patients that selling or giving away this medication is against the law.
- Advise patients that, after SUBOXONE has completely dissolved in the oral mucosa, to take a sip of water, swish it gently around their teeth and gums, and swallow. Advise patients to wait for at least one hour after taking SUBOXONE before brushing teeth [see Warnings and Precautions (5.13)].
- Refer patients to dental care services and encourage them to have regular dental checkups while taking SUBOXONE. Instruct patients to inform their dentist that they have started therapy on SUBOXONE [see Warnings and Precautions (5.13)].
- Caution patients that SUBOXONE sublingual film may impair the mental or physical abilities required for the performance of potentially dangerous tasks such as driving or operating machinery. Caution should be taken especially during drug induction and dose adjustment and until individuals are reasonably certain that buprenorphine therapy does not adversely affect their ability to engage in such activities [see Warnings and Precautions (5.15)].
- Advise patients not to change the dosage of SUBOXONE sublingual film without consulting their healthcare provider.
- Advise patients to take SUBOXONE sublingual film once a day.
- Advise patients that if they miss a dose of SUBOXONE sublingual film they should take it as soon as they remember. If it is almost time for the next dose, they should skip the missed dose and take the next dose at the regular time.
- Inform patients that SUBOXONE sublingual film can cause drug dependence and that withdrawal signs and symptoms may occur when the medication is discontinued.
- Advise patients seeking to discontinue treatment with buprenorphine for opioid dependence to work closely with their healthcare provider on a tapering schedule and inform them of the potential to relapse to illicit drug use associated with discontinuation of opioid agonist/partial agonist medication-assisted treatment.
- Advise patients that, like other opioids, SUBOXONE sublingual film may produce orthostatic hypotension in ambulatory individuals [see Warnings and Precautions (5.16)].
- Advise patients to inform their healthcare provider if any other prescription medications, over-the-counter medications, or herbal preparations are prescribed or currently being used [see Drug Interactions (7)].
- Advise women that if they are pregnant while being treated with SUBOXONE sublingual film, the baby may have signs of withdrawal at birth and that withdrawal is treatable [see Warnings and Precautions (5.5), Use in Specific Populations (8.1)].
- Advise women who are breastfeeding to monitor the infant for drowsiness and difficulty breathing [see Use in Specific Populations (8.2)].
- Inform patients that chronic use of opioids may cause reduced fertility. It is not known whether these effects on fertility are reversible [see Use in Specific Populations (8.3)].
- Advise patients to inform their family members that, in the event of emergency, the treating healthcare provider or emergency room staff should be informed that the patient is physically dependent on an opioid and that the patient is being treated with SUBOXONE sublingual film.

© 2025 Indivior UK Limited | SUBOXONE® and SUBUTEX® are registered trademarks of Indivior UK Limited or its affiliate companies. | All rights reserved.

Manufactured for Indivior Inc. North Chesterfield, VA 23235 by: Aquestive Therapeutics, Warren, NJ 07059

MEDICATION GUIDE
SUBOXONE (Sub-OX-own) (buprenorphine and naloxone) Sublingual Film, CIII

IMPORTANT: Keep SUBOXONE sublingual film in a secure place away from children. Accidental use by a child is a medical emergency and can result in death. If a child accidentally takes SUBOXONE sublingual film, get emergency help or call 911 right away. Tell your healthcare provider if you are living in a household where there are small children.

What is the most important information I should know about SUBOXONE sublingual film?

- SUBOXONE contains a medicine called buprenorphine. Buprenorphine is an opioid that can cause serious and life-threatening breathing problems, especially if you take or use certain other medicines or drugs.
- Ask your healthcare provider about medicines like naloxone or nalmefene that can be used in an emergency to reverse opioid overdose, including accidental use of SUBOXONE sublingual film by a child. If naloxone or nalmefene is given, you must call 911 or get emergency medical help right away to treat an overdose or accidental use of an opioid.
- SUBOXONE may cause serious and life-threatening breathing problems. Get emergency help right away if you:

- feel faint
- feel dizzy
- are confused
- feel sleepy or uncoordinated

- have blurred vision
- have slurred speech
- are breathing slower than normal
- cannot think well or clearly

- Do not take SUBOXONE with certain medicines. Taking SUBOXONE with other opioid medicines, benzodiazepines, gabapentinoids (gabapentin or pregabalin), alcohol, or other central nervous system depressants (including street drugs) can cause severe drowsiness, decreased awareness, breathing problems, coma, and death.
- Do not inject (“shoot-up”) SUBOXONE. Injecting SUBOXONE may cause life-threatening infections and other serious health problems. Injecting SUBOXONE may cause sudden serious withdrawal symptoms such as pain, cramps, vomiting, diarrhea, anxiety, sleep problems, and cravings.
- Do not switch from SUBOXONE sublingual film to other medicines that contain buprenorphine without talking with your healthcare provider. The amount of buprenorphine in a dose of SUBOXONE sublingual film is not the same as in other medicines that contain buprenorphine. Your healthcare provider will prescribe a starting dose of SUBOXONE sublingual film that may be different than other buprenorphine containing medicines you may have been taking.
- Do not stop taking SUBOXONE suddenly. You could become sick and have withdrawal symptoms because your body has become used to the medicine (physical dependence). Physical dependence is not the same as drug addiction.
- In an emergency, have family members tell emergency department staff that you are physically dependent on an opioid and are being treated with SUBOXONE sublingual film.
- Never give anyone else your SUBOXONE sublingual film. They could die from taking it. Selling or giving away SUBOXONE sublingual film is against the law.
- Store SUBOXONE sublingual film securely, out of sight and reach of children, and in a location not accessible by others, including visitors to the home.

What is SUBOXONE sublingual film?

- SUBOXONE sublingual film is a prescription medicine used to treat opioid addiction in adults and is part of a complete treatment program that also includes counseling and behavioral therapy.

Who should not take SUBOXONE sublingual film?
Do not take SUBOXONE sublingual film if you are allergic to buprenorphine or naloxone.

Before taking SUBOXONE, tell your healthcare provider about all your medical conditions, including if you have:

- trouble breathing or lung problems
- a curve in your spine that affects your breathing
- Addison's disease

- an enlarged prostate (men)
- problems urinating
- liver, kidney, or gallbladder problems
- alcoholism

- a head injury or brain problem
- mental health problems
- adrenal gland or thyroid gland problems
- tooth problems, including a history of cavities

Tell your healthcare provider if you are:

- pregnant or plan to become pregnant. If you take SUBOXONE while pregnant, your baby may have symptoms of opioid withdrawal at birth that could be life-threatening if not recognized and treated. Talk to your healthcare provider if you are pregnant or plan to become pregnant.
- Breastfeeding or plan to breastfeed. SUBOXONE can pass into your breast milk and harm your baby. Talk to your healthcare provider about the best way to feed your baby if you take SUBOXONE. Monitor your baby for increased drowsiness and breathing problems if you breastfeed during treatment with SUBOXONE.

Tell your healthcare provider about all the medicines you take, including prescription and over-the-counter medicines, vitamins, or herbal supplements.

How should I take SUBOXONE sublingual film?
Read the Instructions for Use at the end of this Medication Guide for detailed instructions on how to take SUBOXONE

- Take SUBOXONE sublingual film exactly as prescribed by your healthcare provider. Your healthcare provider may change your dose after seeing how it affects you. Do not change your dose unless your healthcare provider tells you to change it.
- Do not take SUBOXONE sublingual film more often than prescribed by your healthcare provider.
- SUBOXONE is not for occasional or “as needed” use.
- When you are beginning treatment, take SUBOXONE sublingual film only under the tongue (sublingual administration).
- After SUBOXONE is completely dissolved, rinse your mouth with water and swallow. Wait for at least one hour before brushing teeth.
- Report any problems with your teeth immediately to your healthcare provider and schedule an appointment with a dentist. Tell your dentist that you have started taking SUBOXONE.
- After a few days, you can choose whether you will take SUBOXONE sublingual film on the inside of your cheek (buccal administration) or under the tongue (sublingual administration).
- Take the entire SUBOXONE sublingual film. Do not cut, tear, chew, or swallow SUBOXONE sublingual film because the medicine will not work as well.
- If you miss a dose of SUBOXONE, take it as soon as you remember. If it is almost time for your next dose, skip the missed dose and take the next dose at your regular time. Do not take 2 doses at the same time unless your healthcare provider tells you to. If you are not sure about your dosing, call your healthcare provider.
- Dispose of expired, unwanted, or unused SUBOXONE by removing SUBOXONE from the foil packaging, and promptly flushing down the toilet (if a drug take-back option is not readily available). Visit www.fda.gov/drugdisposal for additional information on disposal of unused medicines.
- If you take too much SUBOXONE or overdose, call Poison Control or get emergency medical help right away.

What should I avoid while taking SUBOXONE sublingual film?

- Do not drive, operate heavy machinery, or perform any other dangerous activities until you know how SUBOXONE affects you. Buprenorphine can cause drowsiness and slow reaction times. SUBOXONE can make you sleepy, dizzy, or lightheaded.
- You should not drink alcohol or take prescription or over-the-counter medicines that contain alcohol while taking SUBOXONE sublingual film, because this can lead to loss of consciousness or even death.

What are the possible side effects of SUBOXONE sublingual film?
SUBOXONE sublingual film can cause serious side effects, including:

- Trouble breathing. Taking SUBOXONE with other opioid medicines, benzodiazepines, gabapentinoids (gabapentin or pregabalin), alcohol, or other central nervous system depressants (including street drugs) can cause breathing problems that can lead to coma and death.
- Sleepiness, dizziness, and problems with coordination.
- Physical dependence or abuse.
- Liver problems. Call your healthcare provider right away if you notice any of these symptoms:

- your skin or the white part of your eyes turns yellow (jaundice)
- dark or “tea-colored” urine
- light colored stools (bowel movements)

- loss of appetite
- pain, aching, or tenderness on the right side of your stomach area
- nausea

- Your healthcare provider should do blood tests to check your liver before you start taking and while you take SUBOXONE.
- Allergic reaction. You may have a rash, hives, swelling of your face, wheezing, low blood pressure, or loss of consciousness. Call your healthcare provider or get emergency help right away.
- Opioid withdrawal. Call your healthcare provider right away if you get any of these symptoms:

- shaking
- sweating more than normal
- feeling hot or cold more than normal
- runny nose
- watery eyes

- goose bumps
- diarrhea
- vomiting
- muscle aches

- Decrease in blood pressure. You may feel dizzy if you get up too fast from sitting or lying down.
- The most common side effects of SUBOXONE include:

- headache
- nausea
- vomiting
- constipation

- pain
- increased sweating
- decrease in sleep (insomnia)

- SUBOXONE sublingual film may affect fertility in males and females. Talk to your healthcare provider if this is a concern for you.

These are not all the possible side effects of SUBOXONE.
Call your doctor for medical advice about side effects. You may report side effects to FDA at 1-800-FDA-1088.

General information about the safe and effective use of SUBOXONE sublingual film.
Medicines are sometimes prescribed for purposes other than those listed in a Medication Guide. Do not take SUBOXONE sublingual film for a condition for which it was not prescribed. Do not give SUBOXONE sublingual film to other people, even if they have the same symptoms you have. It may harm them and it is against the law.
You can ask your doctor or pharmacist for information that is written for healthcare professionals.

© 2025 Indivior UK Limited |SUBOXONE® is a registered trademark of Indivior UK Limited or its affiliate companies. | All rights reserved.
Manufactured for Indivior Inc., North Chesterfield, VA 23235 by Aquestive Therapeutics, Warren, NJ 07059
For more information, go to www.SUBOXONE.com or call 1-877-782-6966.

This Medication Guide has been approved by the U.S. Food and Drug Administration.

Revised: 12/2025

INSTRUCTIONS FOR USE

SUBOXONE (Sub-OX-own) (buprenorphine and naloxone) Sublingual Film, CIII

This “Instructions for Use” contains information on how to correctly take SUBOXONE sublingual film.

Important Information You Need to Know Before Taking SUBOXONE sublingual film:

- Your healthcare provider should show you how to take SUBOXONE sublingual film the right way.
- Each SUBOXONE sublingual film comes in a sealed child‐resistant foil pouch. Do not open the foil pouch until you are ready to take it.

Preparing to take SUBOXONE sublingual film:

- To open your SUBOXONE sublingual film foil pouch, fold along the dotted line (see Figure 1).
  Figure 1
- Tear down at slit or cut with scissors along the arrow (see Figure 2).
  Figure 2
- Before taking SUBOXONE sublingual film, drink water to moisten your mouth. This helps the film dissolve more easily.

To take SUBOXONE sublingual film under your tongue (sublingual administration):

- Hold the film between two fingers by the outside edges.
- Place the SUBOXONE sublingual film under your tongue, close to the base either to the left or right of the center (see Figure 3).
  Figure 3
- If your healthcare provider tells you to take 2 films at a time, place the second film under your tongue on the opposite side. Avoid letting the films touch.
- Keep the films in place until they have completely dissolved.
- If your healthcare provider tells you to take a third film, place it under your tongue on either side after the first 2 films have dissolved.

To take SUBOXONE sublingual film on the inside of your cheek (buccal administration):

- Hold the film between two fingers by the outside edges.
- Place one film on the inside of your right or left cheek (see Figure 4).
  Figure 4
  - If your healthcare provider tells you to take 2 films at a time, place the other film on the inside of the opposite cheek.
  - Keep the films in place until they have completely dissolved.
  - If your healthcare provider tells you to take a third film, place it on the inside of your right or left cheek after the first 2 films have dissolved.
- While SUBOXONE sublingual film is dissolving, do not chew or swallow the film because the medicine will not work as well.
- Talking while the film is dissolving can affect how well the medicine in SUBOXONE sublingual film is absorbed.
- After SUBOXONE is completely dissolved, rinse your mouth with water and swallow. Wait for at least one hour before brushing teeth.
- If you miss a dose of SUBOXONE sublingual film, take your medicine when you remember. If it is almost time for your next dose, skip the missed dose and take the next dose at your regular time. Do not take 2 doses at the same time unless your healthcare provider tells you to. If you are not sure about your dosing, call your healthcare provider.
- Do not stop taking SUBOXONE sublingual film suddenly. You could become sick and have withdrawal symptoms because your body has become used to the medicine. Physical dependence is not the same as drug addiction. Your healthcare provider can tell you more about the differences between physical dependence and drug addiction. To have fewer withdrawal symptoms, ask your healthcare provider how to stop using SUBOXONE sublingual film the right way.

If you take too much SUBOXONE sublingual film or overdose, call Poison Control or get emergency medical help right away.

Storing SUBOXONE Sublingual Film:

- Store SUBOXONE sublingual film at room temperature between 68°F to 77°F (20°C to 25°C).
- Keep SUBOXONE sublingual film in a safe place, out of the sight and reach of children.

Disposing of SUBOXONE Sublingual Film:

- Dispose of unused SUBOXONE sublingual film as soon as you no longer need them.
- Dispose of expired, unwanted or unused SUBOXONE sublingual film by removing the SUBOXONE sublingual film from the foil packaging, and promptly flushing down the toilet (if a drug take-back option is not readily available). Do not flush the SUBOXONE sublingual film foil pouch down the toilet. Visit www.fda.gov/drugdisposal for additional information on disposal of unused medicines.

If you need help with disposal of SUBOXONE sublingual film, call 1‐877‐782‐6966.

SUBOXONE® is a registered trademark of Indivior UK Limited.

This “Instructions for Use” has been approved by the U.S. Food and Drug Administration.
Revised 06/2022

Principal Display Panel – 2 mg Carton Label

NDC 12496-1202-3

2 mg/0.5 mg CIII

30 pouches each containing
1 sublingual film

Suboxone®
(buprenorphine and naloxone) sublingual film

2 mg/0.5 mg

Rx only

Children who accidentally take SUBOXONE will
need emergency medical care. Keep SUBOXONE
out of the reach of children.

Do not cut, chew or
swallow sublingual film.

suboxone.com

Principal Display Panel – 4 mg Carton Label

NDC 12496-1204-3

4 mg/1 mg CIII

30 pouches each containing
1 sublingual film

Suboxone®
(buprenorphine and naloxone) sublingual film

4 mg/1 mg

Rx only

Children who accidentally take SUBOXONE will
need emergency medical care. Keep SUBOXONE
out of the reach of children.

Do not cut, chew or
swallow sublingual film.

suboxone.com

Principal Display Panel – 8 mg Carton Label

NDC 12496-1208-3

8 mg/2 mg CIII

30 pouches each containing
1 sublingual film

Suboxone®
(buprenorphine and naloxone) sublingual film

8 mg/2 mg

Rx only

Children who accidentally take SUBOXONE will
need emergency medical care. Keep SUBOXONE
out of the reach of children.

Do not cut, chew or
swallow sublingual film.

suboxone.com

Principal Display Panel –12 mg Carton Label

NDC 12496-1212-3

12 mg/3 mg CIII

30 pouches each containing
1 sublingual film

Suboxone®
(buprenorphine and naloxone) sublingual film

12 mg/3 mg

Rx only

Children who accidentally take SUBOXONE will
need emergency medical care. Keep SUBOXONE
out of the reach of children.

Do not cut, chew or
swallow sublingual film.

suboxone.com